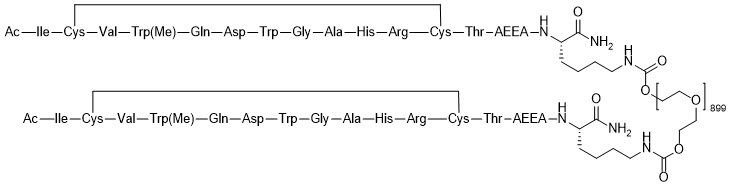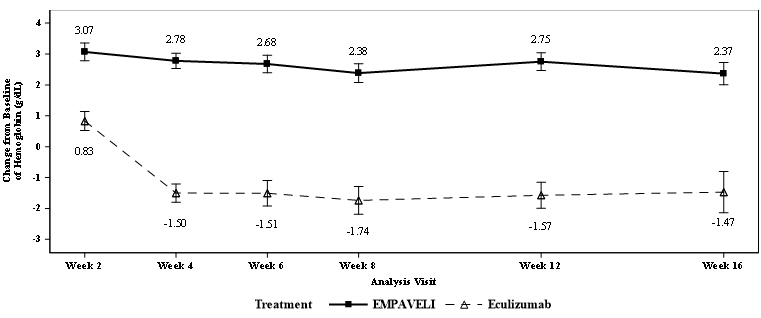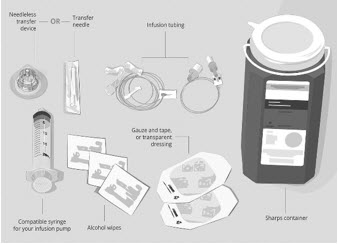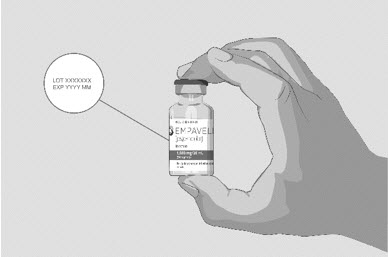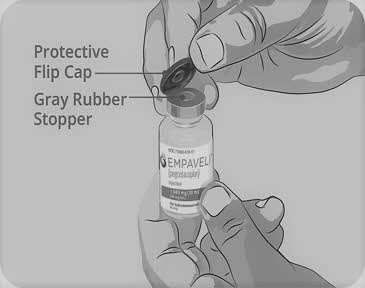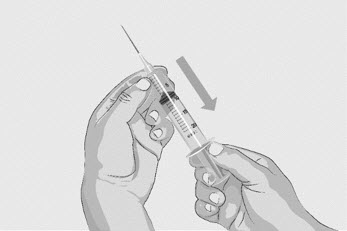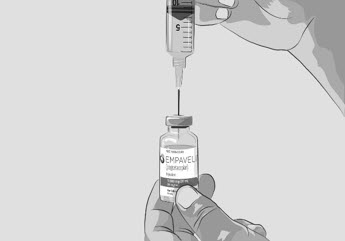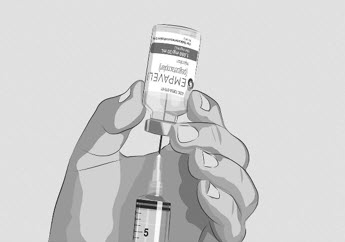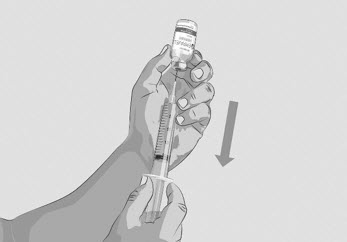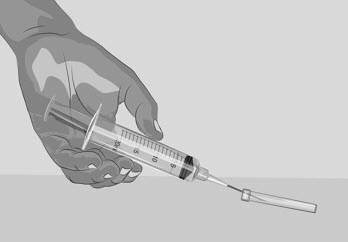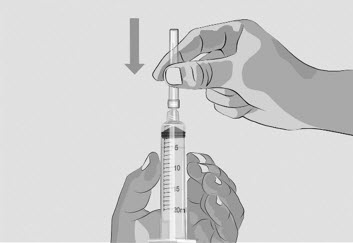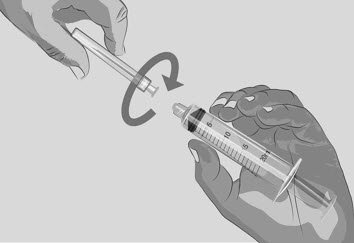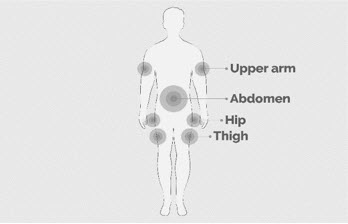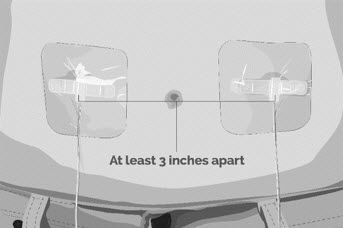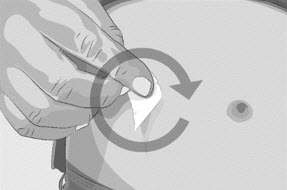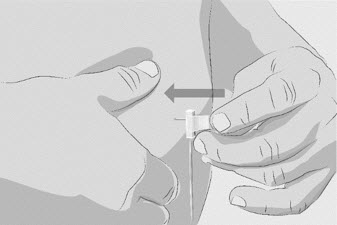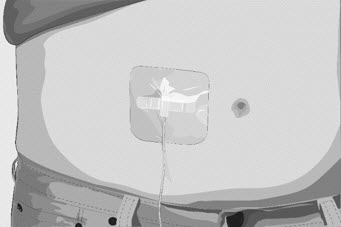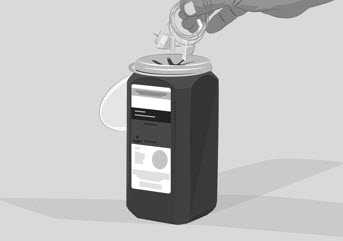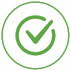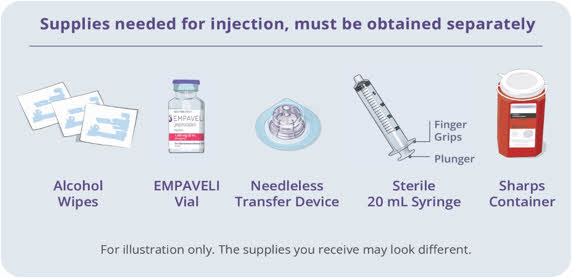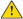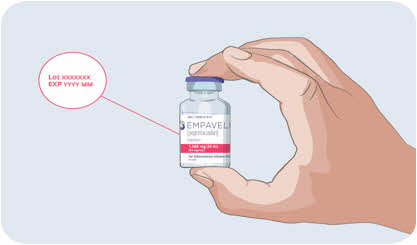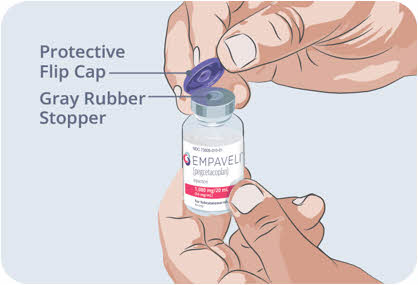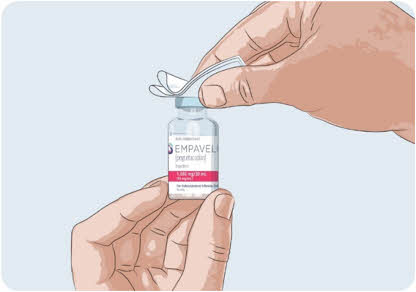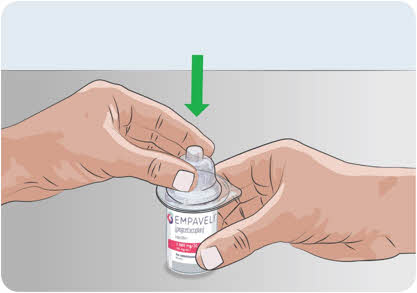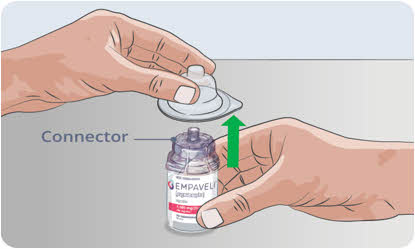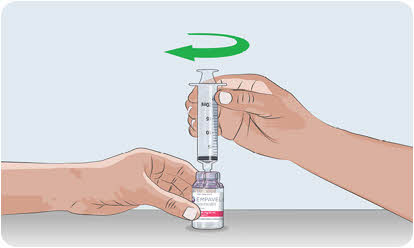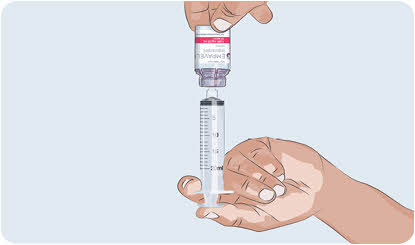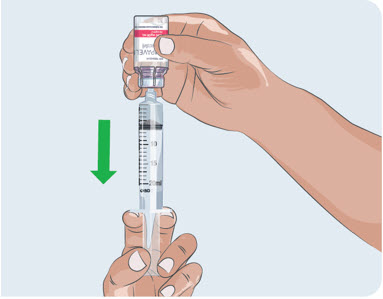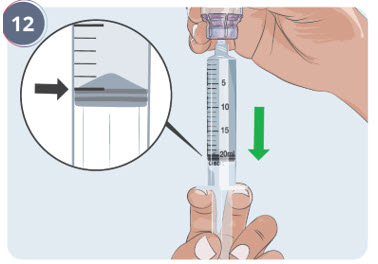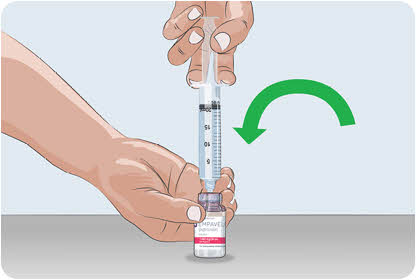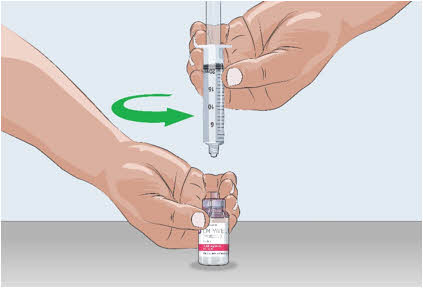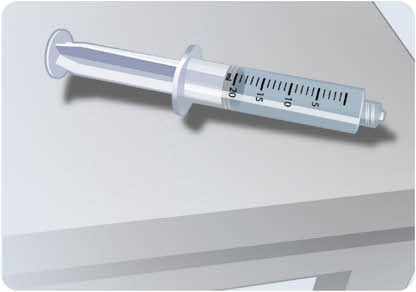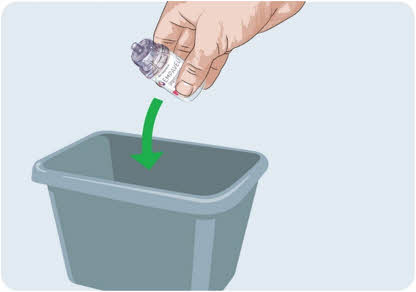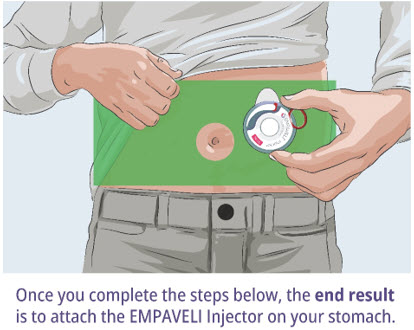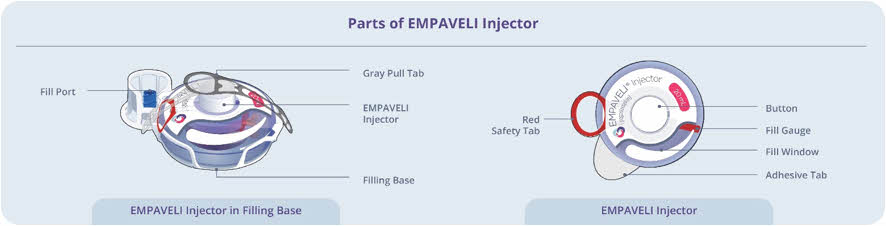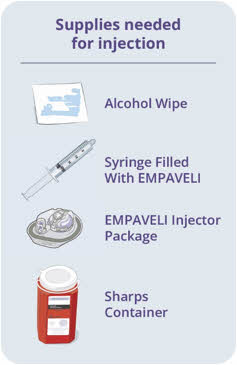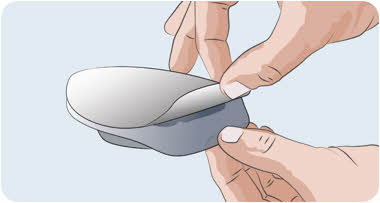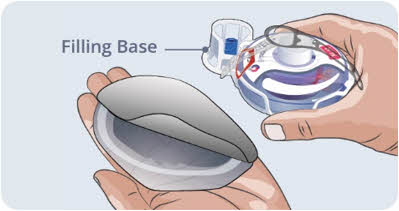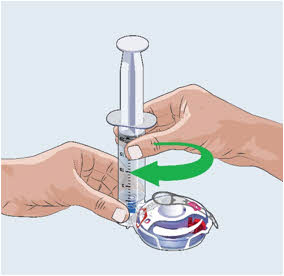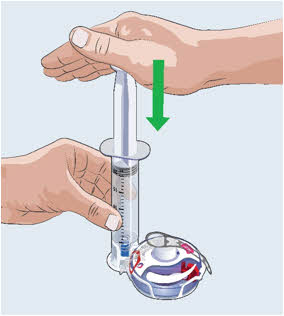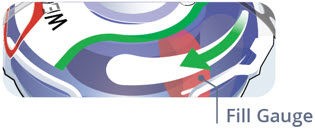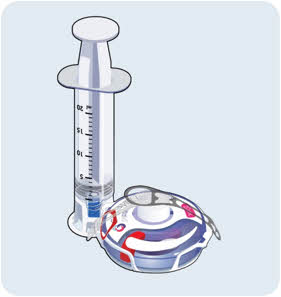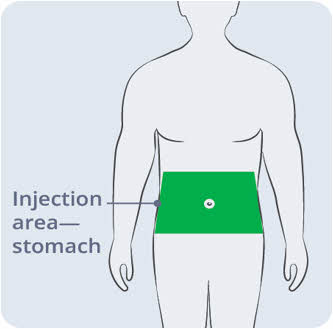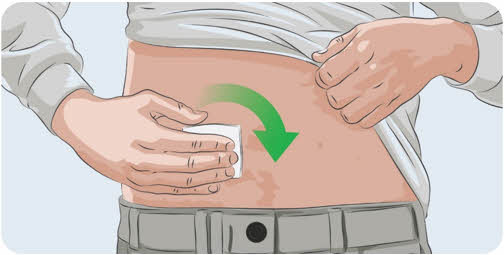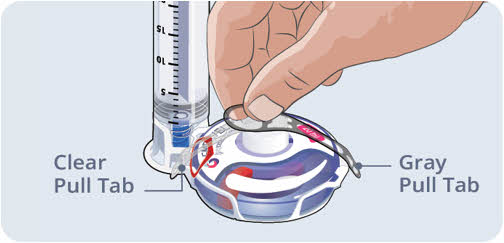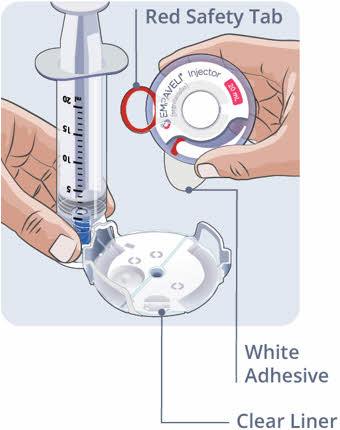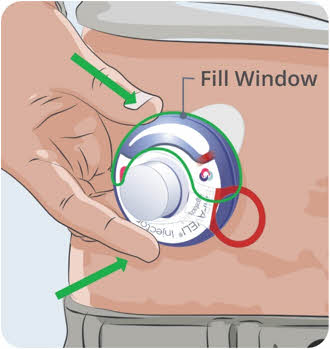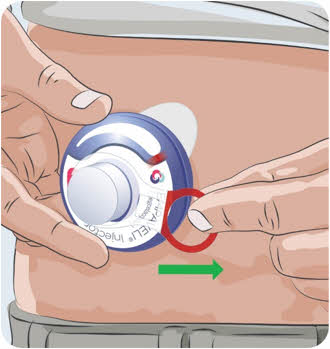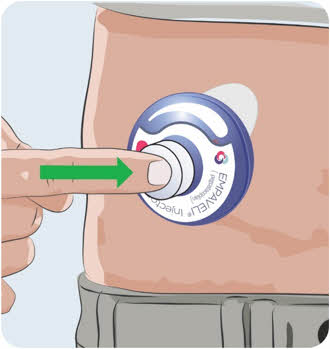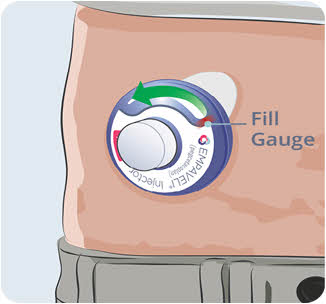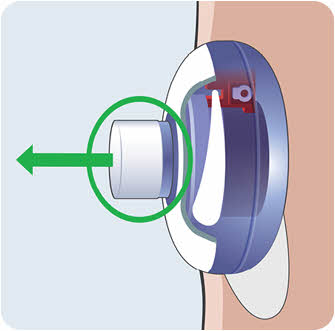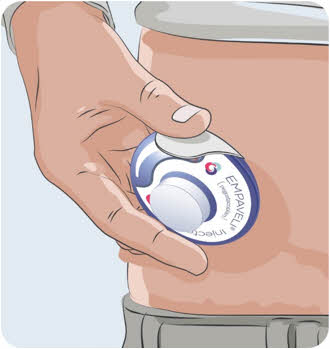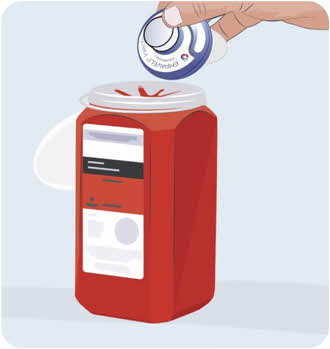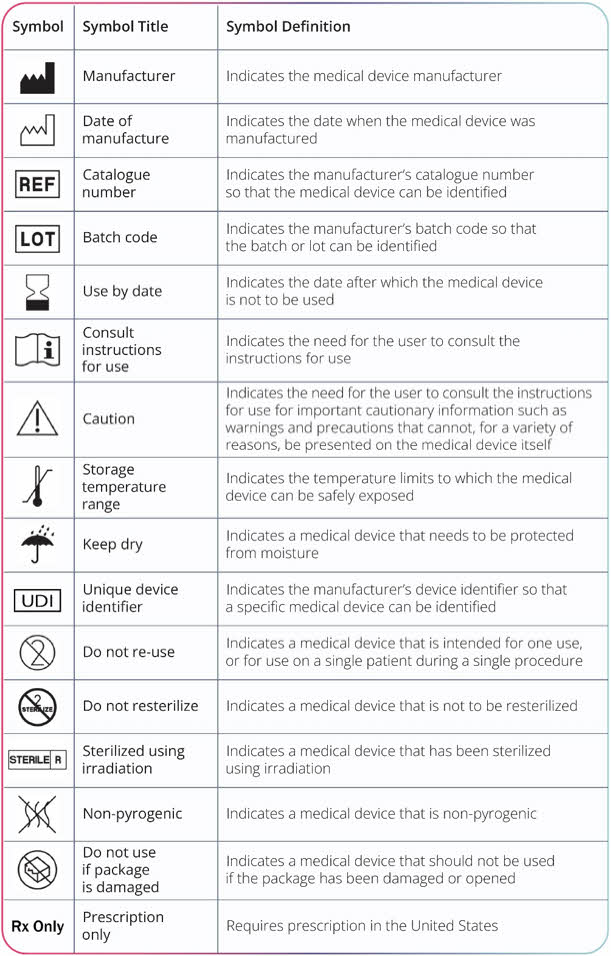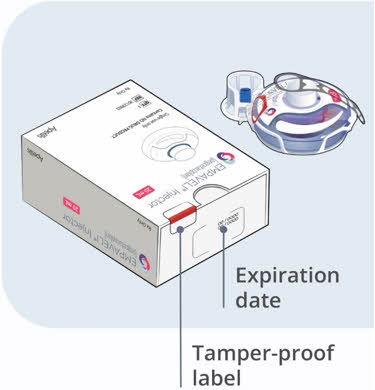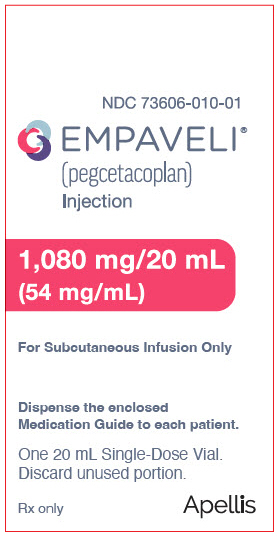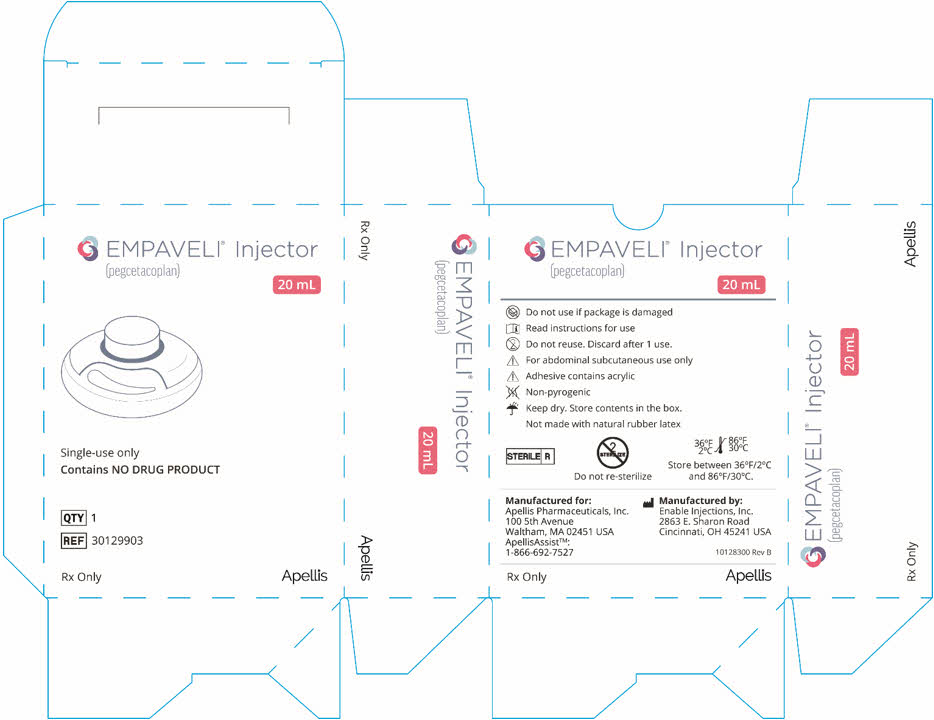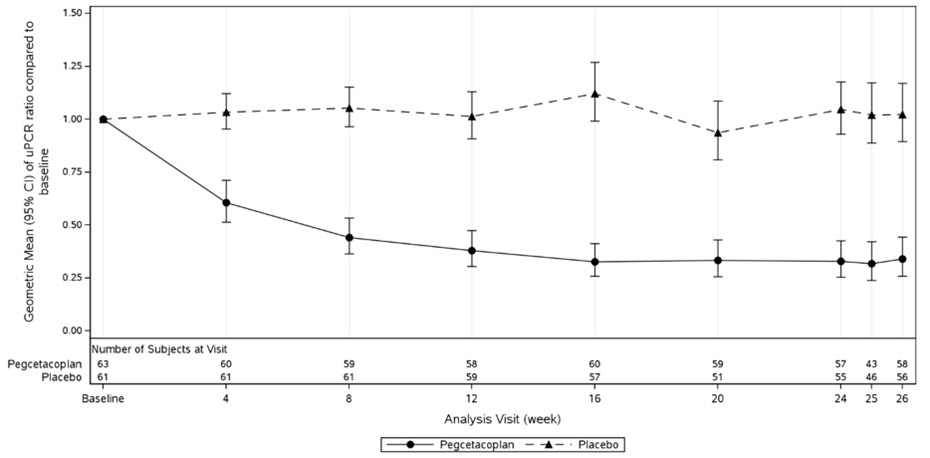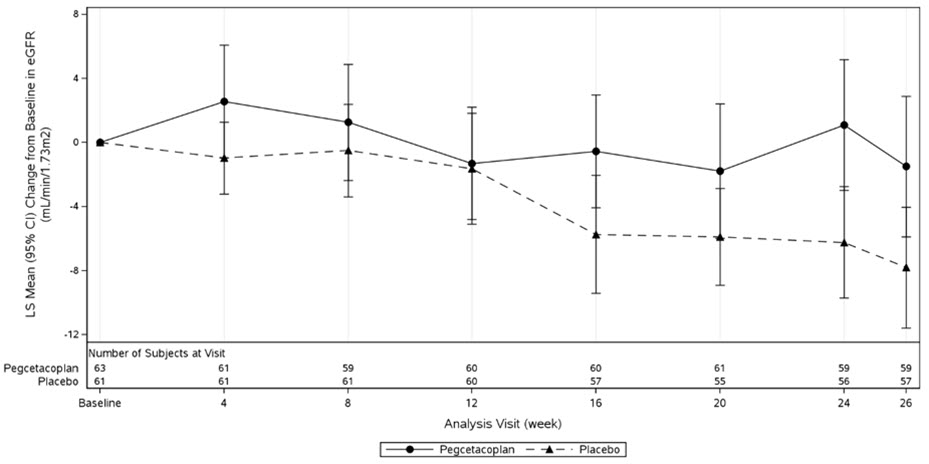 DRUG LABEL: Empaveli
NDC: 73606-010 | Form: INJECTION, SOLUTION
Manufacturer: Apellis Pharmaceuticals, Inc.
Category: prescription | Type: HUMAN PRESCRIPTION DRUG LABEL
Date: 20250730

ACTIVE INGREDIENTS: Pegcetacoplan 1080 mg/20 mL
INACTIVE INGREDIENTS: SORBITOL 820 mg/20 mL; ACETIC ACID; SODIUM ACETATE; SODIUM HYDROXIDE; WATER

HIGHLIGHTS OF PRESCRIBING INFORMATION

These highlights do not include all the information needed to use EMPAVELI safely and effectively. See full prescribing information for EMPAVELI.
EMPAVELI® (pegcetacoplan) injection, for subcutaneous use
Initial U.S. Approval: 2021

WARNING: SERIOUS INFECTIONS CAUSED BY ENCAPSULATED BACTERIA

See full prescribing information for complete boxed warning.

EMPAVELI increases the risk of serious and life-threatening infections caused by encapsulated bacteria including Streptococcus pneumoniae, Neisseria meningitidis and Haemophilus influenzae type B.

- Complete or update vaccination for encapsulated bacteria at least 2 weeks prior to the first dose of EMPAVELI, unless the risks of delaying EMPAVELI outweigh the risks of developing a serious infection. Comply with the most current Advisory Committee on Immunization Practices (ACIP) recommendations for vaccinations against encapsulated bacteria in patients receiving a complement inhibitor. (5.1)
- Patients receiving EMPAVELI are at increased risk for invasive disease caused by encapsulated bacteria, even if they develop antibodies following vaccination. Monitor patients for early signs and symptoms of serious infections and evaluate immediately if infection is suspected. (5.1)

EMPAVELI is available only through a restricted program called EMPAVELI REMS.

RECENT MAJOR CHANGES

Indication (1.2) | 7/2025
Dosage and Administration (2.3) | 7/2025
Warnings and Precautions (5.3) | 7/2025

1 INDICATIONS AND USAGE

EMPAVELI is a complement inhibitor indicated:

- for the treatment of adult patients with paroxysmal nocturnal hemoglobinuria (PNH). (1.1)
- for the treatment of adult and pediatric patients aged 12 years and older with C3 glomerulopathy (C3G) or primary immune-complex membranoproliferative glomerulonephritis (IC-MPGN), to reduce proteinuria. (1.2)

2 DOSAGE AND ADMINISTRATION

PNH (2.2)

Recommended dosage is 1,080 mg administered subcutaneously twice weekly.

C3G or Primary IC-MPGN (2.3)

- Recommended dosage for adults is 1,080 mg administered subcutaneously twice weekly.
- Recommended dosage for pediatric patients is dependent upon patient weight. See full prescribing information for the recommended dosage in patients with C3G or IC-MPGN. (2.2)
- EMPAVELI can be administered via a commercially available pump or with EMPAVELI Injector. (2.4)
- See Full Prescribing Information for instructions on preparation and administration. (2.2, 2.3, 2.4)

3 DOSAGE FORMS AND STRENGTHS

- Injection: 1,080 mg/20 mL (54 mg/mL) in a single-dose vial. (3)

4 CONTRAINDICATIONS

EMPAVELI is contraindicated:

- in patients with hypersensitivity to pegcetacoplan or any of the excipients. (4)
- for initiation in patients with unresolved serious infection caused by encapsulated bacteria. (4)

5 WARNINGS AND PRECAUTIONS

- Serious infections caused by encapsulated bacteria. (5.1)
- Infusion-Related Reactions: Monitor patients for infusion-related reactions and institute appropriate medical management as needed. (5.3)
- Interference with Laboratory Tests: Use of silica reagents in coagulation panels may result in artificially prolonged activated partial thromboplastin time (aPTT). (5.5)

6 ADVERSE REACTIONS

- The most common adverse reactions in patients with PNH (incidence ≥10%) were injection site reactions, infections, diarrhea, abdominal pain, respiratory tract infection, pain in extremity, hypokalemia, fatigue, viral infection, cough, arthralgia, dizziness, headache, and rash. (6.1)
- The most common adverse reactions in patients with C3G or primary IC-MPGN (incidence ≥10%) were infusion site reactions, pyrexia, nasopharyngitis, influenza, cough, and nausea. (6.1)

To report SUSPECTED ADVERSE REACTIONS, contact Apellis Pharmaceuticals, Inc. at 1-833-866-3346 or FDA at 1-800-FDA-1088 or www.fda.gov/medwatch.

FULL PRESCRIBING INFORMATION

WARNING: SERIOUS INFECTIONS CAUSED BY ENCAPSULATED BACTERIA

EMPAVELI, a complement inhibitor, increases the risk of serious infections, especially those caused by encapsulated bacteria, such as Streptococcus pneumoniae, Neisseria meningitidis, and Haemophilus influenzae type B [see Warnings and Precautions (5.1)]. Life-threatening and fatal infections with encapsulated bacteria have occurred in patients treated with complement inhibitors. These infections may become rapidly life-threatening or fatal if not recognized and treated early.

- Complete or update vaccination for encapsulated bacteria at least 2 weeks prior to the first dose of EMPAVELI, unless the risks of delaying therapy with EMPAVELI outweigh the risk of developing a serious infection. Comply with the most current Advisory Committee on Immunization Practices (ACIP) recommendations for vaccinations against encapsulated bacteria in patients receiving a complement inhibitor. See Warnings and Precautions (5.1) for additional guidance on the management of the risk of serious infections caused by encapsulated bacteria.
- Patients receiving EMPAVELI are at increased risk for invasive disease caused by encapsulated bacteria, even if they develop antibodies following vaccination. Monitor patients for early signs and symptoms of serious infections and evaluate immediately if infection is suspected.

Because of the risk of serious infections caused by encapsulated bacteria, EMPAVELI is available only through a restricted program under a Risk Evaluation and Mitigation Strategy (REMS) called the EMPAVELI REMS [see Warnings and Precautions (5.2)].

1 INDICATIONS AND USAGE

1.1 Paroxysmal Nocturnal Hemoglobinuria

EMPAVELI® is indicated for the treatment of adult patients with paroxysmal nocturnal hemoglobinuria (PNH).

1.2 C3 glomerulopathy or primary immune-complex membranoproliferative glomerulonephritis

EMPAVELI® is indicated for the treatment of adult and pediatric patients aged 12 years and older with C3 glomerulopathy (C3G) or primary immune-complex membranoproliferative glomerulonephritis (IC-MPGN), to reduce proteinuria.

2 DOSAGE AND ADMINISTRATION

2.1 Recommended Vaccination and Prophylaxis

Vaccinate patients against encapsulated bacteria, including Streptococcus pneumoniae and Neisseria meningitidis (serogroups A, C, W, Y and B), according to current ACIP recommendations at least 2 weeks prior to initiation of EMPAVELI therapy [see Warnings and Precautions (5.1)].

If urgent EMPAVELI therapy is indicated in a patient who is not up to date with vaccines for Streptococcus pneumoniae and Neisseria meningitidis, according to ACIP recommendations, provide the patient with antibacterial drug prophylaxis and administer these vaccines as soon as possible.

Healthcare professionals who prescribe EMPAVELI must enroll in the REMS for EMPAVELI [see Warnings and Precautions (5.2)].

2.2 Recommended Dosage - PNH

The recommended dose of EMPAVELI is 1,080 mg administered subcutaneously twice weekly [see Dosage and Administration (2.4)].

Dosage for patients switching to EMPAVELI from C5 inhibitors

To reduce the risk of hemolysis with abrupt treatment discontinuation:

- For patients switching from eculizumab, initiate EMPAVELI while continuing eculizumab at its current dose. After 4 weeks, discontinue eculizumab before continuing on monotherapy with EMPAVELI.
- For patients switching from ravulizumab, initiate EMPAVELI no more than 4 weeks after the last dose of ravulizumab.

Dose Adjustment

- For lactate dehydrogenase (LDH) levels greater than 2 × the upper limit of normal (ULN), adjust the dosing regimen to 1,080 mg every three days.
- In the event of a dose increase, monitor LDH twice weekly for at least 4 weeks.

Missed Dose

- Administer EMPAVELI as soon as possible after a missed dose. Resume the regular dosing schedule following administration of the missed dose.

2.3 Recommended Dosage - C3G or Primary IC-MPGN

For adults (18 years and older)

The recommended dose of EMPAVELI is 1,080 mg (20 mL) administered subcutaneously twice weekly [see Dosage and Administration (2.4)].

For pediatric patients (12 years to less than 18 years of age)

For pediatric patients 12 years of age and older, administer EMPAVELI dose and volume based upon body weight, according to the schedule in Table 1. Administer the recommended dose of EMPAVELI subcutaneously twice weekly [see Dosage and Administration (2.4)] .

Table 1: Dosing recommendation in C3G or primary IC-MPGN
Patient Body Weight | First dose (infusion volume) | Second dose (infusion volume) | Maintenance dose (infusion volume)
50 kg or higher | 1,080 mg (20 mL) | 1,080 mg (20 mL) | 1,080 mg twice weekly (20 mL)
35 kg to less than 50 kg | 648 mg (12 mL) | 810 mg (15 mL) | 810 mg twice weekly (15 mL)
Less than 35 kg | 540 mg (10 mL) | 540 mg (10 mL) | 648 mg twice weekly (12 mL)

Missed Dose

Administer EMPAVELI as soon as possible after a missed dose. Resume the regular dosing schedule following administration of the missed dose.

2.4 Administration

EMPAVELI is for subcutaneous administration using:

- A commercially available infusion pump with a reservoir of at least 20 mL OR
- EMPAVELI Injector, a single-use, disposable on body injector

EMPAVELI is intended for use under the guidance of a healthcare professional. Patients may self-administer or caregivers may administer EMPAVELI after proper training by a healthcare professional on how to prepare and administer EMPAVELI.

Follow the steps below and use aseptic technique to prepare and administer EMPAVELI, either by an infusion pump or EMPAVELI Injector:

- Prior to use‚ allow EMPAVELI to reach room temperature 20°C to 25°C (68°F to 77°F) for approximately 30 minutes. Keep the vial in the carton until ready for use to protect from light.
- Parenteral drug products should be inspected visually for particulate matter and discoloration prior to administration, whenever solution and container permit. EMPAVELI is a clear, colorless to slightly yellowish solution. Do not use if the liquid looks cloudy, contains particles, or is dark yellow.
- Discard any unused portion of EMPAVELI.

Preparation with Infusion Pump

- Refer to the EMPAVELI Instructions for Use and the infusion pump manufacturer's instructions for full preparation and administration information.
- Use a needleless transfer device (such as a vial adapter) or a transfer needle to fill the syringe.
- Rotate infusion sites (i.e., abdomen, thighs, hips, upper arms) from one infusion to the next. Do not infuse where the skin is tender, bruised, red, or hard. Avoid infusing into tattoos, scars, or stretch marks.
- If multi-infusion sets are needed, ensure the infusion sites are at least 3 inches apart.
- The typical infusion time is approximately 30 minutes (if using two infusion sites) or approximately 60 minutes (if using one infusion site).

Preparation with EMPAVELI Injector

- Refer to the EMPAVELI Injector Instructions for Use, which comes with the device.
- Use a needleless transfer device (such as a vial adapter).
- EMPAVELI Injector is for abdominal subcutaneous use only. Rotate the site of each subcutaneous administration. Do not inject where the skin is tender, bruised, red, or hard. Avoid injecting into tattoos, scars, or stretch marks.
- Injection time is approximately 30 to 60 minutes.

3 DOSAGE FORMS AND STRENGTHS

Injection: 1,080 mg/20 mL (54 mg/mL) clear, colorless to slightly yellowish solution in a single-dose vial.

4 CONTRAINDICATIONS

EMPAVELI is contraindicated:

- in patients with hypersensitivity to pegcetacoplan or to any of the excipients [see Warnings and Precautions (5.3)].
- for initiation in patients with unresolved serious infection caused by encapsulated bacteria including Streptococcus pneumoniae, Neisseria meningitidis, and Haemophilus influenzae type B [see Warnings and Precautions (5.1)].

5 WARNINGS AND PRECAUTIONS

5.1 Serious Infections Caused by Encapsulated Bacteria

EMPAVELI, a complement inhibitor, increases a patient's susceptibility to serious, life-threatening, or fatal infections caused by encapsulated bacteria including Streptococcus pneumoniae, Neisseria meningitidis (caused by any serogroup, including non-groupable strains), and Haemophilus influenzae type B. Life-threatening and fatal infections with encapsulated bacteria have occurred in both vaccinated and unvaccinated patients treated with complement inhibitors. The initation of EMPAVELI treatment is contraindicated in patients with unresolved serious infection caused by encapsulated bacteria.

Complete or update vaccination against encapsulated bacteria at least 2 weeks prior to administration of the first dose of EMPAVELI, according to the most current ACIP recommendations for patients receiving a complement inhibitor. Revaccinate patients in accordance with ACIP recommendations considering the duration of therapy with EMPAVELI. Note that, ACIP recommends an administration schedule in patients receiving complement inhibitors that differs from the administration schedule in the vaccine prescribing information. If urgent EMPAVELI therapy is indicated in a patient who is not up to date with vaccines against encapsulated bacteria according to ACIP recommendations, provide the patient with antibacterial drug prophylaxis and administer these vaccines as soon as possible. Various durations and regimens of antibacterial drug prophylaxis have been considered, but the optimal durations and drug regimens for prophylaxis and their efficacy have not been studied in unvaccinated or vaccinated patients receiving complement inhibitors, including EMPAVELI. The benefits and risks of treatment with EMPAVELI, as well as the benefits and risks of antibacterial drug prophylaxis in unvaccinated or vaccinated patients, must be considered against the known risks for serious infections caused by encapsulated bacteria.

Vaccination does not eliminate the risk of serious encapsulated bacterial infections, despite development of antibodies following vaccination. Closely monitor patients for early signs and symptoms of serious infection and evaluate patients immediately if an infection is suspected. Inform patients of these signs and symptoms and instruct patients to seek immediate medical care if these signs and symptoms occur. Promptly treat known infections. Serious infection may become rapidly life-threatening or fatal if not recognized and treated early. Consider interruption of EMPAVELI in patients who are undergoing treatment for serious infections.

EMPAVELI is available only through a restricted program under a REMS [see Warnings and Precautions (5.2)].

5.2 EMPAVELI REMS

EMPAVELI is available only through a restricted program under a REMS called EMPAVELI REMS, because of the risk of serious infections caused by encapsulated bacteria [see Warnings and Precautions (5.1)].

Notable requirements of the EMPAVELI REMS include the following:

- Prescribers must enroll in the REMS.
- Prescribers must counsel patients about the risk of serious infections caused by encapsulated bacteria.
- Prescribers must provide the patients with the REMS educational materials.
- Prescribers must assess patient vaccination status for encapsulated bacteria and vaccinate if needed according to current ACIP recommendations two weeks prior to the first dose of EMPAVELI.
- Prescribers must provide a prescription for antibacterial drug prophylaxis if treatment must be started urgently, and the patient is not up to date with vaccinations against encapsulated bacteria according to current ACIP recommendations at least two weeks prior to the first dose of EMPAVELI.
- Pharmacies that dispense EMPAVELI must be certified in the EMPAVELI REMS and must verify prescribers are certified.
- Patients must receive counseling from the prescriber about the need to receive vaccinations against encapsulated bacteria per ACIP recommendations, the need to take antibiotics as directed by the prescriber, and the signs and symptoms of serious infections.
- Patients must be instructed to carry the Patient Safety Card with them at all times during and for 2 months following treatment discontinuation with EMPAVELI.

Further information is available at www.empavelirems.com or 1-888-343-7073

5.3 Infusion-Related Reactions

Systemic hypersensitivity reactions (e.g., facial swelling, rash, urticaria, pyrexia) have occurred in patients treated with EMPAVELI, which may resolve after treatment with antihistamines. Cases of anaphylaxis leading to treatment discontinuation have been reported. If a severe hypersensitivity reaction (including anaphylaxis) occurs, discontinue EMPAVELI infusion immediately, institute appropriate treatment, per standard of care, and monitor until signs and symptoms are resolved.

5.4 Monitoring PNH Manifestations after Discontinuation of EMPAVELI

After discontinuing treatment with EMPAVELI, closely monitor for signs and symptoms of hemolysis, identified by elevated LDH levels along with sudden decrease in PNH clone size or hemoglobin, or reappearance of symptoms such as fatigue, hemoglobinuria, abdominal pain, dyspnea, major adverse vascular events (including thrombosis), dysphagia, or erectile dysfunction. Monitor any patient who discontinues EMPAVELI for at least 8 weeks to detect hemolysis and other reactions. If hemolysis, including elevated LDH, occurs after discontinuation of EMPAVELI, consider restarting treatment with EMPAVELI.

5.5 Interference with Laboratory Tests

There may be interference between silica reagents in coagulation panels and EMPAVELI that results in artificially prolonged activated partial thromboplastin time (aPTT); therefore, avoid the use of silica reagents in coagulation panels.

6 ADVERSE REACTIONS

The following clinically significant adverse reactions are discussed in greater detail in other sections of the labeling:

- Serious Infections Caused by Encapsulated Bacteria [see Warnings and Precautions (5.1)]
- Infusion-Related Reactions [see Warnings and Precautions (5.3)]

6.1 Clinical Trials Experience

Because clinical trials are conducted under widely varying conditions, adverse reaction rates observed in the clinical trials of a drug cannot be directly compared to rates in the clinical trials of another drug and may not reflect the rates observed in practice.

Paroxysmal Nocturnal Hemoglobinuria

Study in Complement-Inhibitor Experienced Adult Patients with PNH (Study APL2-302)

The data described below reflect the exposure in 80 adult patients with PNH who received EMPAVELI (n=41) or eculizumab (n=39) at the recommended dosing regimens for 16 weeks. Serious adverse reactions were reported in 7 (17%) patients with PNH receiving EMPAVELI. The most common serious adverse reaction in patients treated with EMPAVELI was infections (5%). The most common adverse reactions (≥10%) with EMPAVELI were injection-site reactions, infections, diarrhea, abdominal pain, respiratory tract infection, viral infection, and fatigue.

Table 2 describes the adverse reactions that occurred in ≥5% of patients treated with EMPAVELI in Study APL2-302.

Table 2: Adverse Reactions Reported in ≥5% of Patients Treated with EMPAVELI in Study APL2-302
Adverse Reaction | EMPAVELI (N=41) n (%) | Eculizumab (N=39) n (%)
General disorders and administration site conditions
Injection-site reaction [Grouped terms] [Term includes injection-site erythema, injection-site reaction, injection-site swelling, injection-site induration, injection-site bruising, injection-site pain, injection-site pruritus, vaccination site reaction, administration site swelling, injection-site hemorrhage, injection -site edema, injection-site warmth, administration site pain, application site pain, injection-site mass, injection-site rash, vaccination site pain] | 16 (39) | 2 (5)
Fatigue | 5 (12) | 9 (23)
Chest pain | 3 (7) | 1 (3)
Infections and infestations
Infections | 12 (29) | 10 (26)
Respiratory tract infection | 6 (15) | 5 (13)
Viral Infection | 5 (12) | 3 (8)
Gastrointestinal disorders
Diarrhea | 9 (22) | 1 (3)
Abdominal pain | 8 (20) | 4 (10)
Musculoskeletal disorders
Back pain | 3 (7) | 4 (10)
Nervous system disorders
Headache | 3 (7) | 9 (23)
Vascular disorders
Systemic hypertension | 3 (7) | 1 (3)

Clinically relevant adverse reactions in less than 5% of patients include:

- Intestinal ischemia
- Biliary sepsis
- Hypersensitivity pneumonitis

After the randomized control period, 77 patients continued the study, and all were treated with EMPAVELI monotherapy at the recommended dosing regimen for up to 48 weeks. Serious adverse reactions were reported in 18 patients (23%). Additional adverse reactions reported in >5% of patients treated with EMPAVELI during the open-label part of the study compared to the randomized controlled part in Table 1 were cough (12%), arthralgia (8%), oropharyngeal pain (8%), pyrexia (8%), pain in extremity (7%), thrombocytopenia (7%), abdominal distension (5%), acute kidney injury (5%), anxiety (5%), and myalgia (5%). One patient (1%) died due to COVID-19 infection.

Description of Select Adverse Reactions

Injection-Site Reactions

Injection/infusion-site reactions (e.g., erythema, swelling, induration, pruritus, and pain) have been reported during Study APL2-302. These reactions were mild or moderate in severity.

Diarrhea

Seventeen cases of diarrhea have been reported during the 48 weeks. Fifteen of the cases were mild and two were moderate.

Study in Complement-Inhibitor Naïve Adult Patients with PNH (Study APL2-308)

The data described below reflect the exposure in adult patients with PNH who received EMPAVELI (n=46) or the control arm (supportive care excluding complement inhibitors) (n=18) in Study APL2-308 [see Clinical Studies (14.1)]. One patient (2%) who received EMPAVELI died due to septic shock. Serious adverse reactions were reported in 6 (13%) patients with PNH receiving EMPAVELI. The most common adverse reaction (≥10%) in patients treated with EMPAVELI were injection site reactions, infections, viral infection, pain in extremity, hypokalemia, arthralgia, dizziness, abdominal pain, rash, and headache.

Table 3 describes the adverse reactions that occurred in ≥5% of patients treated with EMPAVELI in Study APL2‑308.

Table 3: Adverse Reactions Reported in ≥5% of Patients Treated with EMPAVELI in Study APL2-308
Adverse Reaction | EMPAVELI (N=46) n (%) | Control Arm [Control Arm = supportive care (excluding complement inhibitors)] (N=18) n (%)
Adverse Reaction | Exposure Adjusted Rate (per 100 pt yrs) | Exposure Adjusted Rate (per 100 pt yrs)
General disorders and administration site conditions
Injection-site reaction [Grouped terms] [Term includes injection-site bruising, injection-site hemorrhage, injection-site swelling, application site reaction, infusion-site pruritus, injection-site erythema, injection-site rash, puncture site reaction.] | 12 (26) 42 | 0 0
Pyrexia | 4(9) 14 | 0 0
Peripheral edema | 3 (7) 11 | 0 0
Infections and Infestations
Infections | 9 (20) 32 | 4 (22) 74
Viral infection | 6 (13) 21 | 2 (11) 37
Musculoskeletal and connective tissue disorders
Pain in extremity | 6 (13) 21 | 0 0
Arthralgia | 5 (11) 18 | 0 0
Musculoskeletal pain | 3 (7) 11 | 0 0
Metabolism and nutrition disorders
Hypokalemia | 6 (13) 21 | 2 (11) 37
Nervous system disorders
Dizziness | 5 (11) 18 | 0 0
Headache | 5 (11) 18 | 0 0
Somnolence | 3 (7) 11 | 0 0
Gastrointestinal disorders
Abdominal pain | 5 (11) 18 | 1 (6) 18
Skin and subcutaneous tissue disorders
Rash | 5(11) 18 | 0 0
Ecchymosis | 3 (7) 11 | 0 0
Erythema | 3 (7) 11 | 0 0
Blood and lymphatic system disorders
Thrombocytopenia | 3 (7) 11 | 1 (6) 18
Respiratory, thoracic and mediastinal disorders
Cough | 4 (9) 14 | 0 0
Epistaxis | 3 (7) 11 | 0 0
Investigations
Blood creatinine increased | 3 (7) 11 | 0 0
EMPAVELI (N=46) group includes patients who received EMPAVELI at any point during the study, including patients randomized to EMPAVELI (N=35) and patients randomized to the control arm and crossed over to EMPAVELI treatment (N=11).

C3 Glomerulopathy or Primary IC-MPGN

Study in Adult and Pediatric Patients 12 Years of age and older with C3G or primary IC-MPGN (Study APL2-C3G-310)

The data described below reflects the exposure in adult (n=35) and pediatric patients 12 years of age and older (n=28) with native kidney C3G (n=46), native kidney primary IC-MPGN (n=12), or recurrent C3G following kidney transplant (n=5) who received EMPAVELI at the recommended dosing regimens during the 26-week placebo-controlled period of APL2-C3G-310. Serious adverse reactions due to viral infections resulting in hospitalizations occurred in 2 (3%) patients with C3G or primary IC-MPGN receiving EMPAVELI and 1 (2%) patient on placebo. One patient (2%) on EMPAVELI with native kidney C3G died because of respiratory failure due to COVID-19 pneumonia; there were no deaths in the placebo arm.

Table 4 describes the adverse reactions that were reported in ≥5% of patients (adults and pediatric patients 12 years of age and older) treated with EMPAVELI and at a greater incidence than placebo in APL2-C3G-310. Adverse reactions in pediatric patients were similar to those seen in adults.

The placebo-controlled period of APL2-C3G-310 was followed by a 26-week open-label period. During the open-label period, one patient with native kidney C3G had a serious adverse event of pneumonia secondary to Streptococcus pneumoniae, and one patient with recurrent C3G following kidney transplant developed herpes zoster meningoencephalitis while on concomitant immunosuppression, leading to treatment discontinuation.

Table 4: Adverse Reactions Reported in ≥5% of Patients (adult and pediatric) Treated with EMPAVELI and Greater than Placebo in Study APL2-C3G-310
Adverse Reaction | EMPAVELI (N=63) n (%) | Placebo (N=61) n (%)
General disorders and administration site conditions
Infusion-site reactions [Term includes the following reactions at the infusion site: erythema, pruritus, swelling, bruising, induration, pain, hemorrhage, discomfort, oedema, rash, and hypoaesthesia.] | 16 (25) | 14 (23)
Pyrexia | 12 (19) | 6 (10)
Fatigue | 4 (6) | 1 (2)
Infections and infestations
Nasopharyngitis | 11 (18) | 7 (12)
Influenza | 7 (11) | 3 (5)
Gastrointestinal disorders
Nausea | 6 (10) | 4 (7)
Respiratory, thoracic and mediastinal disorders
Cough | 6 (10) | 1 (2)

Study in Adult recurrent C3G or primary IC-MPGN following kidney transplant (Study APL2-C3G-204)

In a study in 13 adults with recurrent C3G or primary IC-MPGN after kidney transplant (NCT#04572854), one patient with primary IC-MPGN experienced a serious adverse event of Pneumocystis jirovecii pneumonia while on EMPAVELI and concurrent immunosuppressive medications.

6.2 Postmarketing Experience

The following adverse reactions have been identified during post-approval use of EMPAVELI. Because these reactions are reported voluntarily from a population of uncertain size, it is not always possible to reliably estimate their frequency or establish a causal relationship to EMPAVELI exposure.

- Anaphylaxis and urticaria [see Warnings and Precautions (5.3)]

8 USE IN SPECIFIC POPULATIONS

8.1 Pregnancy

Risk Summary

There are insufficient data on EMPAVELI use in pregnant women to inform a drug-associated risk of major birth defects, miscarriage, or adverse maternal or fetal outcomes. There are risks to the mother and fetus associated with untreated PNH in pregnancy (see Clinical Considerations). The use of EMPAVELI may be considered following an assessment of the risks and benefits.

Treatment of pregnant cynomolgus monkeys with pegcetacoplan at a subcutaneous dose of 28 mg/kg/day (2.9 times human exposure based on AUC) from the gestation period through parturition resulted in a statistically significant increase in abortions or stillbirths compared to controls (see Data).

The estimated background risk of major birth defects and miscarriage for the indicated population is unknown. All pregnancies have a background risk of major birth defect, loss, or other adverse outcomes. In the U.S. general population, the estimated background risk of major birth defects and miscarriages in clinically recognized pregnancies is 2% to 4% and 15% to 20%, respectively.

Clinical Considerations

Disease-associated maternal and/or fetal/neonatal risk

PNH in pregnancy is associated with adverse maternal outcomes, including worsening cytopenias, thrombotic events, infections, bleeding, miscarriages and increased maternal mortality, and adverse fetal outcomes, including fetal death and premature delivery.

Data

Animal Data

Animal reproduction studies with pegcetacoplan were conducted in cynomolgus monkeys. Pegcetacoplan treatment of pregnant cynomolgus monkeys at a subcutaneous dose of 28 mg/kg/day (2.9 times human exposure based on AUC) from the gestation period through parturition resulted in a statistically significant increase in abortions and stillbirths compared to controls. No increase in abortions or stillbirths occurred at a dose of 7 mg/kg/day (1.3 times human exposure based on AUC). No maternal toxicity or teratogenic effects were observed in offspring delivered at term. No developmental effects were observed in infants up to 6 months postpartum. Systemic exposure to pegcetacoplan of less than 1% of maternal levels was detected in fetuses from monkeys treated with 28 mg/kg/day from the period of organogenesis through the second trimester.

8.2 Lactation

Risk Summary

It is not known whether pegcetacoplan is secreted in human milk or whether there is potential for absorption and harm to the infant. There are no data on the effects of pegcetacoplan on milk production. Pegcetacoplan is present in milk of lactating monkeys (see Animal Data). Since many medicinal products are secreted into human milk, and because of the potential for serious adverse reaction in a breastfeeding child, breastfeeding should be discontinued during treatment and for 40 days after the last dose.

Data

Animal Data

Pegcetacoplan was detectable in milk of lactating monkeys at less than 1% concentration of serum levels but was not detectable in the serum of nursing infants.

8.3 Females and Males of Reproductive Potential

Contraception

Females

EMPAVELI may cause embryo-fetal harm when administered to pregnant women [see Use in Specific Populations (8.1)]. Pregnancy testing is recommended for females of reproductive potential prior to treatment with EMPAVELI. Advise female patients of reproductive potential to use effective contraception during treatment with EMPAVELI and for 40 days after the last dose.

8.4 Pediatric Use

The safety and effectiveness of EMPAVELI for the treatment of C3G or primary IC-MPGN have been established in pediatric patients aged 12 years and older. Use of EMPAVELI for this indication is supported by evidence from an adequate and well controlled trial that enrolled 55 pediatric patients aged 12 years and older [see Adverse Reactions (6.1), and Clinical Studies (14.2)]. The safety and effectiveness of EMPAVELI in pediatric patients less than 12 years of age with C3G or IC-MPGN have not been established.

Safety and effectiveness of EMPAVELI in pediatric patients with PNH have not been established.

8.5 Geriatric Use

Clinical studies of EMPAVELI did not include sufficient numbers of subjects aged 65 and over to determine whether they respond differently from younger subjects. Other reported clinical experience has not identified differences in responses between geriatric and younger patients.

11 DESCRIPTION

EMPAVELI contains pegcetacoplan, a complement inhibitor. Pegcetacoplan is a symmetrical molecule comprised of two identical pentadecapeptides covalently bound to the ends of a linear 40-kiloDalton (kDa) PEG molecule. The peptide portions of pegcetacoplan contain 1-methyl-L-tryptophan (Trp(Me)) in position 4 and amino(ethoxyethoxy)acetic acid (AEEA) in position 14.

The molecular weight of pegcetacoplan is approximately 43.5 kDa. The molecular formula is C1970H3848N50O947S4. The structure of pegcetacoplan is shown below.

EMPAVELI injection is a sterile, clear, colorless to slightly yellowish aqueous solution for subcutaneous use and is supplied in a 20-mL single-dose vial. Each 1 mL of solution contains 54 mg of pegcetacoplan, 41 mg of sorbitol, 0.384 mg of glacial acetic acid, 0.490 mg of sodium acetate trihydrate, and Water for Injection USP. EMPAVELI may also contain sodium hydroxide and/or additional glacial acetic acid for adjustment to a target pH of 5.

12 CLINICAL PHARMACOLOGY

12.1 Mechanism of Action

Pegcetacoplan binds to complement protein C3 and its activation fragment C3b, thereby regulating the cleavage of C3 and the generation of downstream effectors of complement activation.

In PNH, extravascular hemolysis (EVH) is facilitated by C3b opsonization while intravascular hemolysis (IVH) is mediated by the downstream membrane attack complex (MAC). Pegcetacoplan acts proximally in the complement cascade controlling both C3b-mediated EVH and terminal complement-mediated IVH.

In C3G and primary IC-MPGN, complement dysregulation and overactivation causes deposition of C3 fragments in glomeruli, which contributes to the pathogenesis of C3G and is thought to contribute to the pathogenesis of IC-MPGN. Pegcetacoplan binds C3 and its activation fragment C3b, therefore inhibiting C3 activation, decreasing C3 glomerular fragment deposition, and decreasing C5 convertase activity and subsequent assembly of C5b-9.

12.2 Pharmacodynamics

In patients with PNH administered multiple doses of pegcetacoplan, the mean C3 concentration increased from 94 mg/dL at baseline to 380 mg/dL at Week 16 and sustained through Week 48 (Study APL2-302). In study APL2-308, the mean C3 concentration increased from 95 mg/dL at baseline to 356 mg/dL at Week 26 [see Clinical Studies (14.1)].

The percentage of PNH Type II + III RBCs increased from 66.2% at baseline to 93.9% at Week 16 and sustained through Week 48 (Study APL2-302). In Study APL2-308, the mean percentage of PNH Type II + III RBCs increased from 42.4% at baseline to 90% at Week 26.

The mean percentage of PNH Type II + III RBCs with C3 deposition decreased from 17.8% at baseline to 0.2% at Week 16 and sustained through Week 48 (Study APL2-302). In Study APL2-308, the mean percentage of PNH Type II + III RBCs with C3 deposition decreased from 2.85% at baseline to 0.09% at Week 26.

In patients with C3G or primary IC-MPGN administered pegcetacoplan SC infusion twice weekly, mean (SD) serum C3 levels increased from 62 (48) mg/dL at baseline to 371 (120) mg/dL at Week 26 compared to no change with placebo. Mean (SD) plasma soluble C5b-9 levels decreased from 903 (698) ng/mL at baseline to 290 (249) ng/mL at Week 26 with EMPAVELI compared to no change with placebo. Of patients with evaluable kidney biopsies (n=69), 74% of patients on pegcetacoplan had a decrease in C3 complement staining by at least 2 orders of magnitude from baseline to Week 26 compared to 12% on placebo.

Cardiac Electrophysiology

At the recommended dose of EMPAVELI, no large mean increases in QTc interval (i.e., greater than 20 msec) were observed.

12.3 Pharmacokinetics

In patients with PNH, the serum pegcetacoplan concentrations achieved steady-state approximately 4 to 6 weeks following the first dose. The exposure of pegcetacoplan increased proportionally over a dose range from 45 to 1,440 mg (0.04 to 1.33 times the approved recommended dose). The mean (CV%) trough serum concentration observed at Week 16 was 706 (15.1%) mcg/mL and sustained through Week 48 (Study APL2-302). In Study APL2-308, mean (CV%) trough serum concentration was 744 (25.5%) mcg/mL at Week 26.

In patients with C3G or primary IC-MPGN, serum pegcetacoplan concentrations reached steady state approximately 4 to 8 weeks following twice weekly SC infusion. The mean (CV%) trough serum concentrations ranged between 716 (31%) and 766 (23%) mcg/mL from Week 4 to Week 26.

Absorption

The median Tmax of pegcetacoplan is between 108 and 144 hours (4.5 to 6 days) after a single dose.

Distribution

The mean (CV%) volume of distribution of pegcetacoplan is approximately 3.98 L (32%) in patients with PNH.

The estimated mean (CV%) volume of distribution of pegcetacoplan is approximately 4.79 L (38%) and 4.58 L (29%) in patients with C3G or primary IC-MPGN, respectively.

Elimination

The estimated mean (CV%) of clearance (CL) is 0.36 L/day (30%) and median effective half-life of elimination (t1/2) is 8.6 days in patients with PNH.

The estimated mean (CV%) of clearance (CL) is 0.32 L/day (54%) and median t1/2 is 10.2 days in patients with C3G. The estimated mean (CV%) of clearance (CL) is 0.3 L/day (51%) and median t1/2 is 10.8 days in patients with primary IC-MPGN.

Metabolism

Pegcetacoplan is expected to be metabolized into small peptides and amino acids by catabolic pathways.

Specific Populations

There were no clinically significant differences on the pharmacokinetics of pegcetacoplan based on age (19 to 81 years old), sex, race (Asian vs. non‑Asian), renal impairment, and hepatic function as evaluated by total bilirubin (0.06‑8.8 mg/dL), albumin (1.8‑5.5 g/dL), aspartate aminotransferase (6‑302 IU/L), or alanine aminotransferase (4‑209 IU/L).

In patients with C3G or primary IC-MPGN, there were no clinically significant differences in pharmacokinetics of pegcetacoplan based on age (12 to 74 years old), diagnosis (C3G vs primary IC-MPGN), and urine protein-to-creatinine ratio (UPCR) (133-13300 mg/g).

12.6 Immunogenicity

PNH

There is insufficient information to characterize the anti-drug antibody response to EMPAVELI and the effects of anti-drug antibodies on pharmacokinetics, pharmacodynamics, safety, or effectiveness of pegcetacoplan products in PNH patients.

C3G or primary IC-MPGN

The observed incidence of anti-drug antibodies is highly dependent on the sensitivity and specificity of the assay. Differences in assay methods preclude meaningful comparisons of the incidence of anti-drug antibodies in the study described below with the incidence of anti-drug antibodies in other studies.

During the 26-week placebo-controlled period in Study APL2-C3G-310, 14 of 62 participants (23%) with C3G or primary IC-MPGN randomized to pegcetacoplan developed anti–pegcetacoplan peptide antibodies. Two of 62 participants (3%) developed anti–pegcetacoplan peptide neutralizing antibodies. There was no identified clinically significant effect of anti-drug antibodies on pharmacokinetics, pharmacodynamics, safety, or effectiveness of pegcetacoplan over the treatment duration of 26 weeks.

13 NONCLINICAL TOXICOLOGY

13.1 Carcinogenesis, Mutagenesis, Impairment of Fertility

Long-term animal carcinogenicity studies of pegcetacoplan have not been conducted.

Pegcetacoplan was not mutagenic when tested in an in vitro bacterial reverse mutation (Ames) and was not genotoxic in an in vitro assay in human TK6 cells or in an in vivo micronucleus assay in mice.

Effects of pegcetacoplan on fertility have not been studied in animals. There were no microscopic abnormalities in male or female reproductive organs in toxicity studies in rabbits and monkeys.

13.2 Animal Toxicology and/or Pharmacology

In toxicology studies in rabbits and cynomolgus monkeys, epithelial vacuolation and infiltrates of vacuolated macrophages were observed in multiple tissues, including the renal tubules, following daily subcutaneous doses of pegcetacoplan up to 7 times the human dose. These findings are attributable to uptake of the PEG moieties of pegcetacoplan. Renal degeneration was observed microscopically in rabbits at exposures (Cmax and AUC) less than those for the human dose, and in monkeys at exposures approximately 2.7-fold those for the human dose. The clinical significance of these findings is uncertain.

14 CLINICAL STUDIES

14.1 Paroxysmal Nocturnal Hemoglobinuria

The efficacy and safety of EMPAVELI in patients with PNH were assessed in two open-label, randomized-controlled Phase 3 studies: Study APL2-302 (NCT03500549) and Study APL2-308 (NCT04085601). All patients who completed the studies were eligible to enroll in a separate long-term extension study.

In both studies, patients were vaccinated against Streptococcus pneumoniae, Neisseria meningitidis types A, C, W, Y, and B, and Haemophilus influenzae type B (Hib), either within 2 years prior to Day 1 or within 2 weeks after starting treatment with EMPAVELI. Patients vaccinated after initiation of treatment with EMPAVELI received prophylactic treatment with appropriate antibiotics until 2 weeks after vaccination. In addition, prophylactic antibiotic therapy was administered at the discretion of the investigator in accordance with local treatment guidelines for patients with PNH receiving treatment with a complement inhibitor.

A dose of 1,080 mg twice weekly was used for patients randomized to the EMPAVELI group of each study. If required, the dose of EMPAVELI could be adjusted to 1,080 mg every 3 days. EMPAVELI was administered as a subcutaneous infusion; the infusion time was approximately 20 to 40 minutes.

Study in Complement-Inhibitor Experienced Adult Patients with PNH (Study APL2-302)

The study enrolled patients with PNH who had been treated with a stable dose of eculizumab for at least the previous 3 months and with Hb levels less than 10.5 g/dL.

Eligible patients entered a 4-week run-in period during which they received EMPAVELI 1,080 mg subcutaneously twice weekly in addition to their current dose of eculizumab. Patients were then randomized in a 1:1 ratio to receive either 1,080 mg of EMPAVELI twice weekly or their current dose of eculizumab through the duration of the 16-week randomized controlled period (RCP).

Randomization was stratified based on the number of packed red blood cell (PRBC) transfusions within the 12 months prior to Day -28 (<4; ≥4) and platelet count at screening (<100,000/mm^3; ≥100,000/mm^3). Following completion of the RCP, all patients entered a 32-week open-label period (OLP) and received monotherapy with EMPAVELI. Patients initially randomized to eculizumab entered a second 4-week run-in period during which they received EMPAVELI in addition to eculizumab before continuing on to receive EMPAVELI monotherapy. All patients who completed the 48-week period were eligible to enroll in a separate long-term extension study.

A total of 80 patients were randomized to receive treatment, 41 to EMPAVELI and 39 to eculizumab. Demographics and baseline disease characteristics were generally well balanced between treatment groups (see Table 5). The median times from PNH diagnosis to Day -28 were 6 and 9.7 years, respectively, for EMPAVELI and eculizumab. The baseline mean total PNH RBC clone sizes (Type III) were 47% for EMPAVELI and 50% for eculizumab. Twenty-nine percent and 23% of patients had a history of major adverse vascular events, and 37% and 26% had a history of thrombosis for patients receiving EMPAVELI or eculizumab, respectively. Within 28 days prior to the first dose of EMPAVELI or eculizumab, respectively, 34% and 31% of patients used anti-thrombotic agents (anti-platelet and/or anticoagulants). During Study APL2-302, 37% and 36% of patients on EMPAVELI and eculizumab, respectively, used antithrombotic agents. A total of 38 patients in the group treated with EMPAVELI and 39 patients in the eculizumab group completed the 16-week RCP and continued into the 32-week OLP. Because of adverse reactions of hemolysis, 3 patients were discontinued from the EMPAVELI group during the RCP. Two out of 41 patients in the EMPAVELI group needed the dose adjustment to 1,080 mg every 3 days.

Table 5: Patient Baseline Demographics and Characteristics in Study APL2-302
Parameter | Statistics | EMPAVELI (N=41) | Eculizumab (N=39)
Age (years) | Mean (SD) | 50.2 (16.3) | 47.3 (15.8)
Sex
Female | n (%) | 27 (65.9) | 22 (56.4)
Race
Asian | n (%) | 5 (12.2) | 7 (17.9)
Black or African American | n (%) | 2 (4.9) | 0
White | n (%) | 24 (58.5) | 25 (64.1)
Other | n (%) | 0 | 1 (2.6)
Not reported | n (%) | 10 (24.4) | 6 (15.4)
Ethnicity
Hispanic or Latino | n (%) | 2 (4.9) | 1 (2.6)
Not Hispanic or Latino | n (%) | 29 (70.7) | 32 (82.1)
Not reported | n (%) | 10 (24.4) | 6 (15.4)
Hemoglobin level (g/dL) | Mean (SD) | 8.7 (1.1) | 8.7 (0.9)
Absolute reticulocyte count (10^9 cells/L) | Mean (SD) | 218 (75) | 216 (69.1)
LDH level (U/L) | Mean (SD) | 257.5 (97.7) | 308.6 (284.8)
Number of transfusions in last 12 months prior to Day -28 | Mean (SD) | 6.1 (7.3) | 6.9 (7.7)
<4 | n (%) | 20 (48.8) | 16 (41)
≥4 | n (%) | 21 (51.2) | 23 (59)

The efficacy of EMPAVELI was based on change from baseline to Week 16 (during RCP) in hemoglobin level. Baseline was defined as the average of measurements recorded prior to taking the first dose of EMPAVELI. Supportive efficacy data included transfusion avoidance, defined as the proportion of patients who did not require a transfusion during the RCP, and change from baseline to Week 16 in absolute reticulocyte count (ARC).

EMPAVELI was superior to eculizumab for the change from baseline in hemoglobin level at Week 16 (p<0.0001). The adjusted mean change from baseline in hemoglobin level was 2.37 g/dL in the group treated with EMPAVELI versus -1.47 g/dL in the eculizumab group (Figure 1), demonstrating an adjusted mean increase of 3.84 g/dL with EMPAVELI compared to eculizumab at Week 16 (95% CI, 2.33-5.34).

Figure 1: Adjusted Mean (± SE) Change from Baseline to Week 16 in Hemoglobin (g/dL) in Study APL2-302 [Treatment effect estimates from a mixed model are shown. The mixed model contained the categorical effects of treatment, visit, treatment by visit interaction, and stratification factors (transfusion history and platelet count at screening), and the continuous covariate of baseline value.]

Non-inferiority was demonstrated in the endpoints of transfusion avoidance and change from baseline in ARC at Week 16.

The adjusted means, treatment differences, and confidence intervals (CIs) for additional efficacy results are shown in Table 6.

Table 6: Additional Efficacy Results at Week 16 in Study APL2-302
 | EMPAVELI (N=41) | Eculizumab (N=39) | Difference (95% CI)
Transfusion avoidance, n (%) | 35 (85%) | 6 (15%) | 63% [Difference in percentages and 95% CI were based on the stratified Miettinen–Nurminen method.] (48%, 77%)
Change from baseline in ARC (10^9 cells/L), LS [LS = Least square] mean (SE) [SE = Standard error] | -136 (6.5) | 28 (11.9) | -164 (-189.9, -137.3)

Efficacy was generally similar across subgroups based on sex, race, and age.

All 77 patients who completed the RCP entered the 32- week OLP, during which all patients received EMPAVELI, resulting in a total exposure of up to 48 weeks. Between Week 16 and Week 48, 10 patients discontinued the study, all due to adverse reactions, and thirteen patients had a dose adjustment to 1,080 mg every three days. The efficacy results at Week 48 were generally consistent with those at Week 16.

Study in Complement-Inhibitor Naïve Adult Patients with PNH (Study APL2-308)

Study APL2-308 enrolled patients with PNH who had not been treated with any complement inhibitor within 3 months prior to enrollment and with Hb levels less than the lower limit of normal (LLN). Eligible patients were randomized in a 2:1 ratio to receive EMPAVELI or supportive care [excluding complement inhibitors (e.g., transfusions, corticosteroids, supplements such as iron, folate, and vitamin B12), hereafter referred to as the control arm] through the duration of the 26-week treatment period. Randomization was stratified based on the number of packed red blood cell (PRBC) transfusions within the 12 months prior to Day -28 (<4; ≥4). At any point during the study, a patient assigned to the control arm treatment group who had Hb levels ≥2 g/dL below baseline or presented with a PNH associated thromboembolic event was offered cross-over to EMPAVELI for the remainder of the study.

A total of 53 patients were randomized, 35 to EMPAVELI and 18 to the control arm. Demographics and baseline disease characteristics were generally well balanced between treatment groups (see Table 7). The mean times from PNH diagnosis to Day 1 were 5.7 and 5.5 years, respectively, for EMPAVELI and the control arm. The baseline mean total PNH RBC clone sizes (Type III) were 31% for EMPAVELI and 28% for the control arm. In the EMPAVELI group, 2.9% of patients had a history of major adverse vascular events. Two patients (5.7%) in the EMPAVELI group and 3 patients (16.7%) in the control arm group had a history of at least 1 type of thrombosis. Within 28 days prior to the first dose of EMPAVELI or the control arm, respectively, 17.1% and 27.8% of patients used anti-thrombotic agents (anti-platelet and/or anticoagulants). During Study APL2-308, 8.6% and 0% of patients on EMPAVELI and the control arm, respectively, used antithrombotic agents. Eleven of 18 patients randomized to the control transitioned to cross-over therapy with EMPAVELI due to a decreased Hb level ≥2 g/dL below baseline. Three patients treated with EMPAVELI required dose adjustment to 1,080 mg every 3 days. Three patients (5.7%; two patients in the EMPAVELI group and one patient in the control arm group) discontinued the study, none due to an adverse reaction.

Table 7: Patient Baseline Demographics and Characteristics in Study APL2-308
Parameter | Statistics | EMPAVELI (N=35) | Control Arm [Control Arm = supportive care (excluding complement inhibitors)]
Parameter | Statistics | EMPAVELI (N=35) | (N=18)
Age (years) | Mean (SD) | 42.2 (12.7) | 49.1 (15.6)
Sex
Female | n (%) | 16 (45.7) | 8 (44.4)
Race
American Indian or Alaska | n (%) | 9 (25.7) | 2 (11.1)
Native
Asian | n (%) | 23 (65.7) | 16 (88.9)
Black or African American | n (%) | 2 (5.7) | 0
Other | n (%) | 1 (2.9) | 0
Ethnicity
Hispanic or Latino | n (%) | 12 (34.3) | 2 (11.1)
Not Hispanic or Latino | n (%) | 23 (65.7) | 16 (88.9)
Hemoglobin level (g/dL) | Mean (SD) | 9.4 (1.4) | 8.7 (0.8)
Absolute reticulocyte count (10^9 cells/L) | Mean (SD) | 230.2 (81) | 180.3 (109.1)
LDH level (U/L) | Mean (SD) | 2151 (909.4) | 1945.9 (1003.7)
Number of transfusions in last 12 months prior to Day -28 | Mean (SD) | 3.9 (4.4) | 5.1 (5)
<4 | n (%) | 21 (60) | 8 (44.4)
≥4 | n (%) | 14 (40) | 10 (55.6)

The efficacy of EMPAVELI was based on the percentage of patients achieving hemoglobin stabilization, defined as avoidance of a >1 g/dL decrease in hemoglobin levels from baseline in the absence of transfusion, and the change from baseline in LDH level. Supportive efficacy data included change from baseline in absolute reticulocyte count (ARC), change from baseline in hemoglobin, and transfusion avoidance, defined as the proportion of patients who did not require a transfusion through Week 26. Baseline was defined as the average of measurements recorded prior to taking the first dose of EMPAVELI or prior to randomization to the control arm treatment group.

Efficacy results are shown in Table 8 below.

Table 8: Efficacy Results During the 26-Week Study in Study APL2-308
 | EMPAVELI (N=35) | Control Arm [Control Arm = supportive care (excluding complement inhibitors)] | Difference (95% CI)
 |  | (N=18) | p-value
Hemoglobin Stabilization [Patients who crossed over from the control arm group to the EMPAVELI group, withdrew from the study, or were lost to follow up are considered as failing to achieve the criteria.] (n, %) | 30 (85.7%) | 0 (0%) | 73% (57%, 89%) p<0.0001 [p-value is obtained by stratified Cochran-Mantel-Haenszel test.]
Change from Baseline in LDH [The post baseline missing values (including the values after cross-over from the control arm) are imputed using a multiple imputation method.] (LS [LS = Least square] Mean CFB, SE [SE = Standard error]) | -1870 (101) | -400 (313) | -1470 (-2113.4, -827.3) p<0.0001
Change from baseline in ARC (LS Mean CFB, SE) | -123 (9.2) | -19 (25.2) | -103 (-158.9, -48.7) p = 0.0002
Change from baseline in Hb (LS Mean CFB, SE) | 2.9 (0.38) | 0.3 (0.76) | 2.7 (0.99, 4.35) p = 0.0019
Transfusion Avoidance (n, %) | 32 (91%) | 1 (6%) | 72% (56%, 89%) p<0.0001
Data collected after cross-over from the control arm is excluded in analyses.

14.2 C3 Glomerulopathy (C3G) or Primary Immune-Complex Membranoproliferative Glomerulonephritis (IC-MPGN)

The efficacy of EMPAVELI in reducing proteinuria in adult and pediatric patients aged 12 years and older with native kidney C3G, native kidney IC-MPGN, or recurrent C3G following kidney transplant was demonstrated in Study APL2-C3G-310. Safety and effectiveness of EMPVAELI in patients with recurrent IC-MPGN following kidney transplant have not been established.

APL2-C3G-310 is a randomized, double-blind, placebo-controlled study that included 124 adult and pediatric patients aged 12 years and older and weighing at least 30 kg with biopsy-proven, native kidney or post-transplant recurrent C3G, or native kidney primary IC-MPGN, eGFR ≥30 mL/min/1.73 m^2, proteinuria ≥1 g/day, and urine protein-to-creatinine ratio (UPCR) ≥1 g/g (NTC 05067127). For at least 12 weeks before randomization and throughout the 26-week placebo-controlled period, patients were required to be on stable and optimized doses of angiotensin-converting enzyme inhibitors, angiotensin receptor blockers and/or sodium-glucose cotransporter-2 (SGLT2) inhibitors. Immunosuppressant medication doses (e.g., steroids no higher than 20 mg daily, mycophenolate mofetil, tacrolimus) had to be stable for at least 12 weeks before randomization and throughout the 26-week placebo-controlled period.

Patients were randomized (1:1) to EMPAVELI or placebo, administered twice weekly as a subcutaneous (SC) infusion for 26 weeks. Randomization was stratified by post-transplant recurrence and by kidney biopsy obtained within 28 weeks of screening. Adults and pediatric patients weighing 50 kg or more received EMPAVELI 1,080 mg (20 mL) twice weekly. Pediatric patients weighing 35 kg to less than 50 kg received 648 mg (12 mL) for the first infusion and 810 mg (15 mL) for each infusion thereafter. Pediatric patients weighing 30 kg to less than 35 kg received EMPAVELI 540 mg (10 mL) for the first 2 infusions and 648 mg (12 mL) twice weekly thereafter.

Patients were vaccinated against Streptococcus pneumoniae, Neisseria meningitidis types A, C, W, Y, and B, and Haemophilus influenzae type B (Hib) at least 14 days prior to randomization, unless documented evidence existed that participants received the recommended vaccinations or were non-responders to vaccination.

At baseline, the mean age was 26 years (range 12 to 74 years); 57% were female, 73% White, 15% Asian, 1% Black or African American, and 11% others. The study population included 55 pediatric patients 12 years to less than 18 years of age; mean age 14.7 years (28 randomized to EMPAVELI and 27 to placebo). Disease type was reasonably balanced between the treatment groups. Overall, 88 patients (71%) had native kidney C3G, 27 patients (22%) had native kidney primary IC-MPGN, and 8 patients (6%) had post-kidney transplant recurrent C3G. At baseline, mean UPCR from triplicate first morning urine (FMU) collections was 3.1 g/g and 2.5 g/g in the pegcetacoplan and placebo groups, respectively; mean eGFR (mL/min/1.73 m^2) was 79 and 87 in the pegcetacoplan and placebo groups, respectively; and mean baseline serum albumin was approximately 3.4 g/dL in both treatment groups.

Approximately 91% of patients were treated with angiotensin-converting enzyme inhibitors (ACEi) or angiotensin II receptor blockers (ARB), 72% with immunosuppressants (e.g., mycophenolate mofetil, tacrolimus), 40% with systemic corticosteroids, and 11% with sodium-glucose co-transporter 2 (SGLT2) inhibitors. Use of each of these medications was balanced between the treatment groups.

The primary efficacy endpoint was the log-transformed ratio of UPCR (sampled from first morning urine collections) at Week 26 compared to baseline. At Week 26, the geometric mean UPCR ratio relative to baseline was 0.33 (95% CI: 0.25, 0.43) and 1.03 (95% CI: 0.91, 1.16) in the EMPAVELI and placebo groups, respectively, resulting in a 68% reduction in UPCR from baseline in the EMPAVELI group compared to placebo (p<0.0001). The treatment effect was consistent across all subgroups including disease type, age, transplant status (C3G), sex, race, baseline disease characteristics (eGFR and UPCR), and immunosuppressant use.

Figure 2 shows the geometric mean UPCR ratio compared to baseline over time.

Figure 2: Geometric Mean of UPCR Ratio Compared to Baseline Over 26 Weeks of Treatment - Study APL2-C3G-310

Abbreviations: FMU = first-morning spot urine;
UPCR = urine protein-to-creatinine ratio.

During the 26-week placebo-controlled period, 49% of patients in the EMPAVELI group achieved a composite renal endpoint defined as a ≥50% reduction in UPCR and stable eGFR (≤15% reduction from baseline) compared with 3% of patients in the placebo group (odds ratio [95% CI] of 27 [6, 124], p<0.0001). Sixty percent of patients in the EMPAVELI group achieved a 50% or greater reduction in UPCR from baseline to Week 26 compared with 5% in the placebo arm, and 68% of patients in the EMPAVELI group had a stable eGFR (≤15% reduction from baseline to Week 26) compared with 59% in the placebo group. Over the first 6 months of treatment, EMPAVELI reduced the loss of kidney function compared to placebo (Figure 3). The efficacy of EMPAVELI in pediatric patients 12 years of age and older was similar to adults.

Figure 3: LS Mean of eGFR Compared to Baseline Over 26 Weeks of Treatment - Study APL2-C3G-310

Abbreviations: LS = least square

LS Mean (95% CI) of difference between EMPAVELI and placebo at Week 26 is 6.31 (0.50, 12.12) mL/min/1.73m^2.

16 HOW SUPPLIED/STORAGE AND HANDLING

How Supplied

EMPAVELI injection is a clear, colorless to slightly yellowish aqueous solution for subcutaneous infusion supplied as 1,080 mg/20 mL (54 mg/mL) solution in 20-mL single-dose vials.

EMPAVELI is available in 20-mL single-dose vials individually packaged in cartons that are supplied in 8-count convenience cartons. NDC 73606-010-01.

Storage and Handling

Store vials of EMPAVELI refrigerated at 2°C to 8°C (36°F to 46°F) in the original carton to protect from light. Do not use beyond the expiration date stamped on the carton.

17 PATIENT COUNSELING INFORMATION

Advise the patient to read the FDA-approved patient labeling (Medication Guide and Instructions for Use).

Dosing

For weight-based dosing, instruct caregivers and patients on the proper techniques for preparing, storing, measuring, and administering EMPAVELI via EMPAVELI Injector or commercially available infusion pump.

Serious Infections Caused by Encapsulated Bacteria

Advise patients of the risk of serious infection. Inform patients of the need to complete or update their vaccinations against encapsulated bacteria at least 2 weeks prior to receiving the first dose of EMPAVELI or receive antibacterial drug prophylaxis if EMPAVELI treatment must be initiated immediately and they have not been previously vaccinated. Inform the patient that they are required to be revaccinated according to current ACIP recommendations for encapsulated bacteria while on EMPAVELI therapy [see Warnings and Precautions (5.1)].

Inform patients that vaccination may not prevent serious infection and strongly advise patients to seek immediate medical attention if these signs or symptoms occur. These signs and symptoms include the following:

- fever with or without shivers or the chills
- fever with chest pain and cough
- fever with breathlessness/fast breathing
- fever with high heart rate
- headache and a fever
- headache with a stiff neck or stiff back
- fever and a rash
- confusion
- headache with nausea or vomiting
- body aches with flu-like symptoms
- clammy skin
- eyes sensitive to light

Inform patients that they will be given a Patient Safety Card for EMPAVELI that they should carry with them at all times. This card describes symptoms which, if experienced, should prompt the patient to seek immediate medical evaluation.

EMPAVELI REMS

EMPAVELI is available only through a restricted program called EMPAVELI REMS [see Warnings and Precautions (5.2)].

Inform the patient of the following notable requirements:

- Patients must receive counseling about the risk of serious infections caused by encapsulated bacteria.
- Patients must receive written educational materials about this risk.
- Patients must be instructed to carry the Patient Safety Card with them at all times during and for 2 months following treatment with EMPAVELI.
- Patients must be instructed to complete or update vaccinations against encapsulated bacteria per ACIP recommendations as directed by the prescriber prior to treatment with EMPAVELI.
- Patients must receive antibiotics as directed by the prescriber if they are not up to date with vaccinations against encapsulated bacteria and have to start EMPAVELI right away.

Anaphylaxis and infusion-related reactions

Advise patients of the risk of anaphylaxis and infusion-related reactions. Inform patients that anaphylaxis is life-threatening and strongly advise patients to seek immediate medical attention if these signs or symptoms occur. These signs and symptoms include the following:

- difficulty breathing including shortness of breath and wheezing
- swollen tongue or throat
- feeling faint
- rapid heart rate
- skin reactions, including hives and itching
- nausea or vomiting
- confusion and anxiety
- dizziness or fainting

Discontinuation

Inform patients with PNH that they may develop hemolysis due to PNH when EMPAVELI is discontinued and that they will be monitored by their healthcare professional for at least 8 weeks following discontinuation of EMPAVELI.

Inform patients who discontinue EMPAVELI to keep the Patient Safety Card with them for 2 months after the last dose of EMPAVELI, because the increased risk of serious infection persists for several weeks following discontinuation of EMPAVELI.

Manufactured for:
Apellis Pharmaceuticals, Inc.
100 Fifth Avenue
Waltham, MA 02451

For patent information: www.apellis.com/productpatent

Copyright © 2025 Apellis Pharmaceuticals, Inc. All rights reserved.

EMPAVELI is a registered trademark of Apellis Pharmaceuticals, Inc.

EMP-PI-28Jul2025-7.0

MEDICATION GUIDE
EMPAVELI® (em-puh-vel-ee)
(pegcetacoplan)
injection, for subcutaneous use

What is the most important information I should know about EMPAVELI?
EMPAVELI is a medicine that affects your immune system. EMPAVELI may lower the ability of your immune system to fight infections.

- EMPAVELI increases your chance of getting serious infections caused by encapsulated bacteria, including Streptococcus pneumoniae, Neisseria meningitidis, and Haemophilus influenzae type B. These serious infections may quickly become life-threatening or cause death if not recognized and treated early.
  - You must complete or be up to date with the vaccines against Streptococcus pneumoniae and Neisseria meningitidis at least 2 weeks before your first dose of EMPAVELI.
  - If you have not completed your vaccines and EMPAVELI must be started right away, you should receive the required vaccines as soon as possible.
  - If you have not been vaccinated and EMPAVELI must be started right away, you should also receive antibiotics to take for as long as your healthcare provider tells you.
  - If you have been vaccinated against these bacteria in the past, you might need additional vaccines before starting EMPAVELI. Your healthcare provider will decide if you need additional vaccines.
  - Vaccines do not prevent all infections caused by encapsulated bacteria. Call your healthcare provider or get emergency medical care right away if you get any of these signs and symptoms of a serious infection:

- fever with or without shivers or the chills
- fever with chest pain and cough
- fever with high heart rate
- headache and fever
- confusion
- clammy skin

- fever and a rash
- fever with breathlessness or fast breathing
- headache with nausea or vomiting
- headache with a stiff neck or stiff back
- body aches with flu-like symptoms
- eyes sensitive to light

Your healthcare provider will give you a Patient Safety Card about the risk of serious infections. Carry it with you at all times during treatment and for 2 months after your last dose of EMPAVELI. Your risk of serious infections may continue for several weeks after your last dose of EMPAVELI. It is important to show this card to any healthcare provider who treats you. This will help them diagnose and treat you quickly.
EMPAVELI is only available through a program called the EMPAVELI Risk Evaluation and Mitigation Strategy (REMS). Before you can take EMPAVELI, your healthcare provider must:

- enroll in the EMPAVELI REMS program
- counsel you about the risk of serious infections caused by certain bacteria
- give you information about the symptoms of serious infections
- make sure that you are vaccinated against serious infections caused by encapsulated bacteria and that you receive antibiotics if you need to start EMPAVELI right away and you are not up to date on your vaccines
- give you a Patient Safety Card about your risk of serious infections, as discussed above
- For more information about side effects, see "What are the possible side effects of EMPAVELI?"

What is EMPAVELI?
EMPAVELI is a prescription medicine used to:

- treat adults with a disease called paroxysmal nocturnal hemoglobinuria (PNH).
- treat adults and children 12 years of age and older with a kidney disease called complement 3 glomerulopathy (C3G) or primary immune-complex membranoproliferative glomerulonephritis (IC-MPGN), to reduce levels of protein in the urine (proteinuria).

It is not known if EMPAVELI is safe and effective in children with PNH.
It is not known if EMPAVELI is safe and effective in children under 12 years of age with C3G or primary IC-MPGN.

Do not take EMPAVELI if you:

- are allergic to pegcetacoplan or any of the ingredients in EMPAVELI. See the end of this Medication Guide for a complete list of ingredients in EMPAVELI.
- have a serious infection caused by encapsulated bacteria, including Streptococcus pneumoniae, Neisseria meningitidis, or Haemophilus influenzae type B when you are starting EMPAVELI treatment.

Before you take EMPAVELI, tell your healthcare provider about all of your medical conditions, including if you:

- have an infection or fever.
- are pregnant or plan to become pregnant. EMPAVELI may harm your unborn baby.
  Females who are able to become pregnant:
  - should have a pregnancy test before starting treatment with EMPAVELI.
  - use an effective method of birth control (contraception) during treatment with EMPAVELI and for 40 days after the last dose.
- are breastfeeding or plan to breastfeed. It is not known if EMPAVELI passes into your breast milk. You should not breastfeed during treatment with EMPAVELI and for 40 days after the last dose.

Tell your healthcare provider about all the medicines you take, including prescription and over-the-counter medicines, vitamins, and herbal supplements. EMPAVELI and other medicines can affect each other, causing side effects.
Know the medicines you take and the vaccines you receive. Keep a list of them to show your healthcare provider and pharmacist when you get a new medicine.

How should I take EMPAVELI?

- See the detailed Instructions for Use that comes with your EMPAVELI for information about how to prepare and infuse your dose of EMPAVELI with your infusion pump.
- See the detailed Instructions for Use that comes with your EMPAVELI Injector for information about how to prepare and inject your dose of EMPAVELI with your EMPAVELI Injector.
- Your healthcare provider should show you how to prepare and administer EMPAVELI before you use it for the first time.
- Use EMPAVELI exactly as your healthcare provider tells you. Do not use more or less than your healthcare provider tells you to.
- If you miss a dose of EMPAVELI, take the missed dose as soon as possible. Take your next dose at your regularly scheduled time.

For adults with PNH:

- EMPAVELI is given under the skin (subcutaneously) 2 times each week. If there is an increase in your LDH, an enzyme in your blood, your healthcare provider may tell you to take EMPAVELI every 3 days.
- If you are changing treatment from eculizumab to EMPAVELI, you should continue eculizumab for 4 weeks after your first dose of EMPAVELI. After 4 weeks, you should stop treatment with eculizumab.
- If you are changing treatment from ravulizumab to EMPAVELI, you should take your starting dose of EMPAVELI no more than 4 weeks after your last dose of ravulizumab.
- If you have PNH and you stop taking EMPAVELI, your healthcare provider will need to monitor you closely for at least 8 weeks after stopping EMPAVELI. Stopping treatment with EMPAVELI may cause a breakdown of red blood cells due to PNH.
  Symptoms or problems that can happen due to red blood cell breakdown include:

- decreased hemoglobin level in your blood
- blood in your urine
- shortness of breath
- trouble swallowing

- tiredness
- pain in the stomach (abdomen)
- blood clots
- erectile dysfunction (ED)

For adults and children 12 years of age and older with C3G or primary IC-MPGN:

- EMPAVELI is given under the skin (subcutaneously) 2 times each week.

What are the possible side effects of EMPAVELI?
EMPAVELI can cause serious side effects including:

- See "What is the most important information I should know about EMPAVELI?"
- Allergic reactions. Allergic reactions can happen during your EMPAVELI infusion and can be life-threatening. Stop your EMPAVELI infusion and get emergency medical care right away if you get any of these symptoms during your EMPAVELI infusion:

- chest pain
- trouble breathing or shortness of breath
- wheezing
- swelling of your face, tongue, or throat
- feel dizzy or faint or pass out

- fast heart rate
- nausea or vomiting
- feel confused or anxious
- skin reactions, including rash, hives, and itching

The most common side effects in adults with PNH treated with EMPAVELI include:

- injection-site reactions
- infections
- diarrhea
- pain in the stomach (abdomen)
- respiratory tract infection
- pain in the arms, hands, legs or feet
- low potassium in blood

- tiredness
- viral infection
- cough
- joint pain
- dizziness
- headache
- rash

The most common side effects in adults and children 12 years of age and older with C3G or primary IC-MPGN treated with EMPAVELI include:

- injection-site reactions
- fever
- common cold

- flu
- cough
- nausea

Tell your healthcare provider about any side effect that bothers you or that does not go away. These are not all of the possible side effects of EMPAVELI.
Call your doctor for medical advice about side effects. You may report side effects to FDA at 1-800-FDA-1088.

How should I store EMPAVELI?

- Store vials of EMPAVELI in the refrigerator between 36°F to 46°F (2°C to 8°C) in the original carton to protect from light.
- Do not use EMPAVELI past the expiration date stamped on the carton.

Keep EMPAVELI and all medicines out of the reach of children.

General information about the safe and effective use of EMPAVELI.
Medicines are sometimes prescribed for purposes other than those listed in a Medication Guide. Do not use EMPAVELI for a condition for which it was not prescribed. Do not give EMPAVELI to other people, even if they have the same symptoms that you have. It may harm them. You can ask your pharmacist or healthcare provider for information about EMPAVELI that is written for health professionals.

What are the ingredients in EMPAVELI?
Active ingredient: pegcetacoplan
Inactive ingredients: sorbitol, glacial acetic acid, sodium acetate trihydrate, Water for Injection USP. EMPAVELI may also contain sodium hydroxide and/or additional glacial acetic acid for pH adjustment.
Manufactured for:
Apellis Pharmaceuticals, Inc. 100 Fifth Avenue Waltham, MA 02451
For patent information: www.apellis.com/productpatent
Copyright © 2025 Apellis Pharmaceuticals, Inc. All rights reserved.
EMPAVELI is a registered trademark of Apellis Pharmaceuticals, Inc.
For more information, go to www.EMPAVELI.com or call 1-866-692-7527.
EMP-MG-28Jul2025-7.0

This Medication Guide has been approved by the U.S. Food and Drug Administration.

Revised: 7/2025

INSTRUCTIONS FOR USE
EMPAVELI® (em-puh-vel-ee)
(pegcetacoplan)
injection, for subcutaneous use
infusion pump

Important Information

This Instructions for Use is for the infusion pump only. If using EMPAVELI Injector, follow the Instructions for Use that comes with the EMPAVELI Injector.

Read this Instructions for Use before you start using EMPAVELI with an infusion pump and each time you get a refill as there may be new information. This information does not take the place of talking to your healthcare provider about your medical condition or treatment. Your healthcare provider should show you or your caregiver how to infuse EMPAVELI the right way before you use it for the first time. Ask your healthcare provider about any instructions you do not understand.

How should I store EMPAVELI?

- Store vials of EMPAVELI in the refrigerator between 36°F to 46°F (2°C to 8°C) in the original carton to protect from light.
- Do not use EMPAVELI past the expiration date stamped on the carton.

Keep EMPAVELI and all medicines out of the reach of children.

Step 1 | Prepare for infusion Before you start:; - Find a well-lit, flat work surface area, like a table. - Remove a single vial carton from the refrigerator. Keep the vial in the carton at room temperature 68°F to 77°F (20°C to 25°C) and allow it to warm up for about 30 minutes. - Do not try to speed up the warming process.
 | Gather your supplies (See Figure A):; - Infusion pump and manufacturer's instructions (not shown) - Compatible syringe for your infusion pump - Transfer needle OR - Needleless transfer device to draw up the medicine from the vial - Infusion set (not shown; varies according to device manufacturer's instructions) - Infusion tubing - Sharps container - Alcohol wipes - Gauze and tape, or transparent dressing | Figure A: Supplies
 | Clean your work surface well using an alcohol wipe.
 | Wash your hands well with soap and water. Dry your hands.
Step 2 | Check the vial and liquid; - Remove the vial from the carton. Carefully look at the liquid in the vial of EMPAVELI. - EMPAVELI is a clear, colorless to slightly yellowish liquid. Check for particles or color changes (See Figure B).; Do not use the vial and call ApellisAssist at 1-866-MY-APL-ASSIST (1-866-692-7527) if:; - The liquid looks cloudy, contains particles, or is dark yellow. - The protective flip cap is missing or damaged. - The expiration date on the label has passed. | Figure B
Step 3 | Prepare and fill syringe; - Remove the protective flip cap from the top of the vial to show the middle part of the gray rubber stopper of the EMPAVELI vial (See Figure C). Throw away the protective flip cap. - Clean the gray rubber stopper with a new alcohol wipe and allow the gray rubber stopper to dry for at least 30 seconds.; Do not touch the exposed gray rubber stopper after wiping. | Figure C
 | Option 1: If using a needleless transfer device (such as a vial adapter), follow the instructions provided by the device manufacturer. OR Option 2: If transfer is done using a transfer needle and a syringe, follow the instructions below:; - Attach a sterile transfer needle to a sterile syringe. - Pull back the plunger to the 20-mL mark to fill the syringe with air (See Figure D). - Push the air-filled syringe with transfer needle attached down through the center of the vial gray rubber stopper. - The tip of the transfer needle should not be in the solution to avoid creating air bubble(s) (See Figure E). - Gently push the air from the syringe into the vial. This will inject the air from the syringe into the vial. | Figure D; Figure E
 | - Turn the vial upside down and insert the transfer needle in the EMPAVELI solution (See Figure F). | Figure F
 | - With the transfer needle tip in the EMPAVELI solution, slowly pull the plunger back to fill the syringe with your prescribed dose (See Figure G). Your first dose, second dose, and maintenance dose may be different. - Double check that you have withdrawn your prescribed dose. - Remove the filled syringe with EMPAVELI and the transfer needle from the vial. - Throw away the vial with the needleless transfer device attached and any remaining EMPAVELI solution into the household trash. | Figure G
 | - Remove the transfer needle by using 1 hand to slide the needle into the needle cap and scoop upwards to cover the needle (See Figure H). | Figure H
 | - After the needle is covered, push the needle cap down towards the syringe to fully attach it with 1 hand to prevent an accidental stick with the needle (See Figure I). | Figure I
 | - Twist off and remove the transfer needle (See Figure J). | Figure J
Step 4 | Prepare infusion pump and tubing; - Gather the infusion pump supplies and follow the device manufacturer's instructions to prepare the pump and tubing.
Step 5 | Prepare the infusion site(s); - Select an area on your stomach (abdomen), thighs, hips, or upper arms for the infusion(s) (See Figure K). Avoid the following infusion areas: - Do not infuse into areas where the skin is tender, bruised, red, or hard. - Avoid infusing into tattoos, scars, or stretch marks. | Figure K
 | - Use a different site(s) from the last time you infused EMPAVELI. If there are multiple infusion sites, they should be at least 3 inches apart. Change (rotate) infusion sites in between each infusion (See Figure L). | Figure L
 | - Clean the skin at each infusion site(s) with a new alcohol wipe, starting at the center of each infusion site and working outward in a circular motion (See Figure M). - Let the skin dry. | Figure M
Step 6 | Insert and secure the infusion needle(s); - Pinch the skin between your thumb and forefinger around the infusion site (where you plan to insert the needle). - Insert the needle into the skin (See Figure N). | Figure N
 | - Secure the needle(s) using gauze and tape or a transparent dressing placed over the infusion site(s) (See Figure O). | Figure O
Step 7 | Start infusion; - Follow the device manufacturer's instructions to start the infusion. - Start the infusion right away after drawing EMPAVELI into the syringe. - EMPAVELI infusion takes about 30 minutes (if using 2 infusion sites) or about 60 minutes (if using 1 infusion site) to complete.
Step 8 | Complete infusion; - Follow the device manufacturer's instructions to complete the infusion.
Step 9 | Record infusion; - Record your treatment as directed by your healthcare provider.
Step 10 | Clean up; - After the infusion is complete, remove the dressing and slowly take out the needle(s). Cover the infusion site with a new dressing. - Remove the infusion set from the pump and throw it away into the sharps container (See Figure P). - Clean and store the infusion pump according to the device manufacturer's instructions.
Step 11 | Dispose of (throw away) used needles and syringes and EMPAVELI infusion tubing.; - Put the used needles, syringes, and EMPAVELI infusion tubing in an FDA-cleared sharps disposal container right away after use (See Figure P). - Do not dispose of (throw away) the used needles, syringes, and EMPAVELI infusion tubing in your household trash. - If you do not have an FDA-cleared sharps disposal container, you may use a household container that is: - made of heavy-duty plastic, - can be closed with a tight-fitting, puncture-resistant lid, without sharps being able to come out, - upright and stable during use, - leak-resistant, and - properly labeled to warn of hazardous waste inside the container. - When your sharps disposal container is almost full, you will need to follow your community guidelines for the right way to dispose of your sharps disposal container. There may be state or local laws about how you should throw away used needles and syringes. - For more information about safe sharps disposal, and for specific information about sharps disposal in the state that you live in, go to the FDA's website at: http://www.fda.gov/safesharpsdisposal. - Do not throw away your used sharps disposal container in your household trash unless your community guidelines permit this. - Do not recycle your used sharps disposal container. | Figure P

Call 1-866-692-7527 to speak with an Apellis representative.
Manufactured for:
Apellis Pharmaceuticals, Inc. 100 Fifth Avenue Waltham, MA 02451
Copyright © 2025 Apellis Pharmaceuticals, Inc. All rights reserved.
EMPAVELI is a registered trademark of Apellis Pharmaceuticals, Inc.

This Instructions for Use has been approved by the U.S. Food and Drug Administration.
Revised 7/2025

EMP-IFU-28Jul2025-5.0

INSTRUCTIONS FOR USE
EMPAVELI® Injector
(pegcetacoplan)
injection, for subcutaneous use
Single-use on-body injector

Important Information
This Instructions for Use is for the EMPAVELI Injector only.

Read this Instructions for Use before you start using the Injector and each time you get a refill as there may be new information. The EMPAVELI Injector is placed on your body to give medicine under the skin. This information does not take the place of talking to your healthcare provider about your medical condition or treatment. Your healthcare provider should show you or your caregiver how to inject EMPAVELI the right way before you use it for the first time. It is important that you do not try to give yourself or someone else the injection unless you have received training from your healthcare provider. Ask your healthcare provider about any instructions you do not understand.

If you have questions, concerns, or need of help, please call ApellisAssist® at 1-866-MY-APL-ASSIST (1-866-692-7527).

SIDE 1:
Filling the Syringe

Start Here
Complete these instructions on how to prepare EMPAVELI before completing EMPAVELI Injector administration instructions on the back of this page.

How should I store EMPAVELI?

- Store vials of EMPAVELI in the refrigerator between 36°F to 46°F (2°C to 8°C) in the original carton to protect from light.
- Do not use EMPAVELI past the expiration date stamped on the carton.

Keep EMPAVELI, EMPAVELI Injector, and all medicines out of the reach of children.

Prepare for injection

1 Before you start:

- Find a well-lit, flat work surface area, like a table.
- Remove a single vial carton of EMPAVELI from the refrigerator. Keep the vial in the carton at room temperature 68°F to 77°F (20°C to 25°C) and allow it to warm up for about 30 minutes.
  Do not try to speed up the warming process.

2

- Wash your hands well with soap and water.
- Dry your hands.

Check the vial and liquid

3

- Remove the vial from the carton. Carefully look at the liquid in the vial of EMPAVELI.
- EMPAVELI is a clear, colorless to slightly yellowish liquid. Check for particles or color changes.

Do not use and call ApellisAssist if:

- The liquid looks cloudy, contains particles, or is dark yellow.
- The protective flip cap is missing from the top of the vial or damaged.
- The expiration date on the label has passed.

4

- Flip up to remove the protective flip cap from the top of the vial to show the exposed middle part of the gray rubber stopper of the EMPAVELI vial.
- Throw away the protective flip cap.

5

- Clean the gray rubber stopper on the top of the EMPAVELI vial with a new alcohol wipe.
- Allow the gray rubber stopper to dry for at least 30 seconds.

Do not touch the exposed gray rubber stopper after wiping.

Prepare and fill the syringe with EMPAVELI using a needleless transfer device (such as a vial adapter)

6
Always follow the Instructions for Use provided by the needleless transfer device's manufacturer (as they may differ from the following steps).

Do not remove the needleless transfer device from the blister package.

Do not touch the spike or the inside of the needleless transfer device.

Do not use the needleless transfer device if it comes out or is dropped out of the package.

Do not use the needleless transfer device if the package is opened.

7

- Remove the cover of the needleless transfer device package.
- Place the vial on a clean, flat surface and hold the vial by the base with one hand.
- Using the outside of the blister package to firmly hold the needleless transfer device, push needleless transfer device straight down onto the vial top until it snaps securely into place.

8

- Remove the blister package from the needleless transfer device and throw the blister package away.

Do not touch the connector at the top of the transfer device.

9

- Remove the syringe from its packaging.

Do not touch the tip of the syringe.

- Attach the syringe to the needleless transfer device by twisting the tip of the syringe to the right (clockwise) onto the top of the needleless transfer device.

10

- Turn the EMPAVELI vial upside down.

11

- Slowly pull the syringe plunger down to about the 5 mL mark to partially fill the syringe.
- Remove air from the syringe by gently pushing on the plunger.

12

- Double check your prescribed dose.
  - Your first dose, second dose and maintenance dose may be different.
- Slowly pull the syringe plunger down to withdraw your prescribed dose of EMPAVELI to the correct marking amount (mL) of medicine that matches the dose your healthcare provider prescribed. Your dose may be different than the example shown.
- Double check that you have withdrawn your prescribed dose. Your dose cannot be changed after it is filled in the EMPAVELI injector.

13

- While holding the EMPAVELI vial and syringe, turn the EMPAVELI vial and filled syringe upright and place the bottom of the EMPAVELI vial on a flat surface.

14

- Remove the filled syringe from the needleless transfer device with one hand while holding the EMPAVELI vial with the other hand and twisting the filled syringe to the left (counterclockwise).

15

- Place the syringe on a clean, flat surface while you prepare the EMPAVELI Injector. The syringe will not leak when set down.

Do not touch the tip of the filled syringe.

16

Do not remove the needleless transfer device from the vial.

- Throw away the vial with the needleless transfer device attached and any remaining EMPAVELI solution into the household trash.

SIDE 2:
Injector Administration

Complete these instructions for administering the EMPAVELI Injector after completing syringe filling instructions on the front of this page.

Important information for administration with EMPAVELI Injector

General use:

- Do not use EMPAVELI Injector if tamper-proof label has been broken.
- Do not use EMPAVELI Injector if you have a skin condition on your stomach (injection site).
- Do not use if you dropped EMPAVELI Injector.
- Do not use if the sealed plastic tray is open or damaged.
- Do not use if the expiration date on the box has passed.
- Do not use if you have an acrylic allergy. Tell your healthcare provider if you are allergic to acrylic.
- Do not reuse EMPAVELI Injector.
- Do not store the filled EMPAVELI Injector.
- Wear loose clothes so that they do not get in the way of the EMPAVELI Injector.
- Do not store the EMPAVELI Injector in direct sunlight. If the EMPAVELI Injector is stored in direct sunlight, do not use it and call ApellisAssist at 1-866-MY-APL-ASSIST (1-866-692-7527).

Using EMPAVELI Injector:

- Do not apply EMPAVELI Injector along the belt line or on areas where the injector will be affected by folds in the skin.
- Do not touch the white adhesive on the bottom of EMPAVELI Injector before attaching to stomach.
- Do not let your clothes touch the clean site.
- Do not remove the Red Safety Tab until EMPAVELI Injector is attached to body.
- Do not remove EMPAVELI Injector from the skin until the button pops out.
- Do not throw away (dispose of) the EMPAVELI Injector into household trash. See the section "Remove and Dispose of EMPAVELI Injector" for information on how to dispose of the EMPAVELI Injector.
- Choose an injection site at least 1 inch from the edge of your belly button and the edge of the EMPAVELI Injector, and 1 inch from last injection site.
- Use the EMPAVELI Injector on stomach only.

During injection:

- Do not remove EMPAVELI Injector from the skin during injection.
- Do not bathe, shower, exercise, use hot tubs, whirlpools, or saunas. Avoid getting your stomach wet. The EMPAVELI Injector is not waterproof. Water or sweat may loosen EMPAVELI Injector from skin.
- Do not sleep or bathe during injection.
- Avoid intense physical activity.
- Do not bump or knock the EMPAVELI Injector.
- Do not bump the EMPAVELI Injector Button.
- Do not use anything to hold the EMPAVELI Injector in place.

Fill injector with EMPAVELI liquid

17

Peel back the cover and remove the clear packaging insert.

Remove the EMPAVELI Injector and the surrounding Filling Base from the packaging. Place it on a clean, flat surface.

18

- Pick up the syringe filled with EMPAVELI.
- Twist the filled syringe tip to the right (clockwise) into the Fill Port until it is tight.

19

- Firmly push the syringe plunger down.
- The syringe plunger may be hard to push.
- Watch the Fill Gauge move as EMPAVELI is pushed into the injector.

20

- Make sure the syringe is empty. If needed, press firmly down on the syringe plunger again.

Do not remove syringe from Filling Base. After the EMPAVELI Injector is filled, continue with the preparation and injection.

Do not store filled EMPAVELI Injector.

Attach EMPAVELI Injector to stomach

21

- Select an area on your stomach to place the EMPAVELI Injector.

Use the EMPAVELI Injector on your stomach only.

- Choose an injection site at least:
  - 1 inch from the edge of your belly button and the edge of the EMPAVELI Injector.
    and
  - 1 inch from your last injection site.

Avoid an injection site that is tender, bruised, red, hard, irritated, scarred, tattooed, or has stretch marks.

Do not apply the EMPAVELI Injector along the belt line or on areas where the EMPAVELI injector will be affected by folds in the skin.

Wear loose clothes so that they do not get in the way of the EMPAVELI Injector.

22

- Clean the injection site with an alcohol wipe.
- Allow the injection site to dry for at least 30 seconds.

Do not let your clothes touch the clean injection site.

23

- Hold the Gray Pull Tab and pull. Allow both the Gray and Clear Pull Tabs to fall to the side.
- Both tabs may fall to the side or come off completely.

Do not remove the Red Safety Tab until the EMPAVELI Injector is attached to the body.

24

- Hold the sides of the EMPAVELI Injector and pull it straight up to remove it from the Filling Base.

Do not touch the adhesive on the bottom of the EMPAVELI Injector or fold the adhesive onto itself.

- The White Adhesive will stay attached to the EMPAVELI Injector and the Clear Liner will stay attached to the Filling Base.

Do not remove the Red Safety Tab until the EMPAVELI Injector is attached to your body.

Ensure the injection site has been cleaned before attaching EMPAVELI Injector.

25

- Position the EMPAVELI Injector so that the Fill Window is pointed up toward your face.
- Press firmly on the clear portion of the EMPAVELI Injector to attach to stomach.

Do not use anything to hold the EMPAVELI Injector in place.

Start Injection

26

- Hold the EMPAVELI Injector with 1 hand. Use the other hand to pull the Red Safety Tab off.
- The EMPAVELI injection will not start until the Red Safety Tab is removed.

27

- Right away, Press the button in firmly until it stays in place to start the EMPAVELI injection.

Pushing the Button in will insert the needle into your skin. You may feel the needle go into your skin.

- Light daily activities can be done during the EMPAVELI injection.

Be careful not to bump or knock the EMPAVELI Injector or button during the EMPAVELI injection.

Keep your stomach dry. Avoid intense physical activity. Do not sleep or bathe during your EMPAVELI injection.

28

- Your EMPAVELI injection will continue as long as the button is pushed in. It may take about 30 to 60 minutes to complete.
- To track progress, watch the Fill Gauge move across Fill Window toward empty. It may take some time to move and may move slowly.

Do not remove the EMPAVELI Injector until the button pops out.

If the button does not pop out after 2 hours (120 minutes), refer to Questions and Answers.

If the EMPAVELI Injector falls off of your body, refer to Questions and Answers.

Caution: Holding down the button will stop the flow of medicine. Injection will begin again when the button is released.

If you have an allergic reaction to the adhesive, call your healthcare provider right away.

29

- When the button pops out, the EMPAVELI injection is done. The needle will be pulled out of the skin and back into the EMPAVELI Injector.

The button popping out is the only way to know if the EMPAVELI injection is complete. Do not remove the EMPAVELI Injector until the Button pops out.

Remove and dispose of EMPAVELI Injector

30

- Use your thumb to lift the Adhesive Tab. Hold the Adhesive Tab against the EMPAVELI Injector.
- Slowly peel the EMPAVELI Injector away from your skin.

31

- Put your used EMPAVELI Injector in an FDA-cleared sharps disposal container right away after use.

Do not throw away the EMPAVELI Injector in the household trash.

The Filling Base with the syringe attached, alcohol wipe, and packaging may be placed in your household trash.

- If you do not have an FDA-cleared sharps disposal container, you may use a household container that is:
  - made of heavy-duty plastic,
  - can be closed with a tight-fitting, puncture-resistant lid, without sharps being able to come out,
  - upright and stable during use,
  - leak-resistant, and
  - properly labeled to warn of hazardous waste inside the container.
- When your sharps disposal container is almost full, you will need to follow your community guidelines for the right way to dispose of your sharps disposal container. There may be state or local laws about how you should throw away used needles and syringes.

- For more information about safe sharps disposal, and for specific information about sharps disposal in the state that you live in, go to the FDA's website at: http:/www.fda.gov/safesharpsdisposal.
- Do not throw away (dispose of) your used sharps disposal container in your household trash unless your community guidelines permit this.
- Do not recycle your used sharps disposal container.
- Keep the used EMPAVELI Injector and sharps disposal container out of the reach of children.

How to store the EMPAVELI Injector

- Keep the EMPAVELI Injector in unopened tray inside the original box.
- Do not open the tray until ready for EMPAVELI injection.
- Store the EMPAVELI Injector unit in clean, dry area away from heat and sunlight, at a temperature between 36°F to 86°F (2°C to 30°C).
- Use the EMPAVELI Injector where the temperature is between 41°F to 104°F (5°C to 40°C).

Questions and answers
Can I use more than 1 syringe to fill the EMPAVELI Injector?
No, use only 1 syringe per EMPAVELI Injector.
What should I do if the syringe plunger will not push down to fill the EMPAVELI Injector?
You must firmly press down on the plunger to fill the EMPAVELI Injector. It will feel like there is resistance.
Can I remove the EMPAVELI Injector from my stomach and put it on later to finish injection?
No. The EMPAVELI Injector cannot be reattached. If you take it off, you may not get your full dose.
How long should the injection take?
The injection time is about 30 to 60 minutes.
After 2 hours (120 minutes):

- If the button has not popped out, press and hold the button while you remove the EMPAVELI Injector from your skin. Do not touch the bottom of the EMPAVELI Injector as the needle will be exposed. Set the EMPAVELI Injector aside
- If you forgot to start the injection, do not push the button. Remove the EMPAVELI Injector and set it aside.

Call ApellisAssist at 1-866-MY-APL-ASSIST (1-866-692-7527) right away after putting your device aside.

What if the Button will not push in and lock?
Make sure that you have taken off the Red Safety Tab. If the Red Safety Tab is removed, make sure you have tried to push the Button in all the way. If you still cannot push the button all the way in, then the EMPAVELI Injector is damaged. Remove your EMPAVELI Injector and set aside. Open a new EMPAVELI Injector and start over. Call ApellisAssist at 1-866-MY-APL-ASSIST (1-866-692-7527).
What if the EMPAVELI Injector falls off of my body?
If the EMPAVELI Injector falls off of your body, pick it up carefully. Do not touch the needle or any medicine that may be on the EMPAVELI Injector. Set the EMPAVELI Injector aside and out of the reach of children. Call ApellisAssist at 1-866-MY-APLASSIST (1-866-692-7527) right away.
Is it normal for skin to be bumpy or irritated during an injection?
No. Your body may be sensitive to the adhesive on the EMPAVELI Injector or to the medicine. Call your healthcare provider right away.
Is it normal for skin to be red after an injection?
Your skin may be slightly red after adhesive removal. If the redness does not go away after 1 to 2 days, call your healthcare provider.

Manufactured for:
Apellis Pharmaceuticals, Inc. 100 Fifth Avenue Waltham, MA 02451

Manufactured by:
Enable Injections, Inc. 2863 E. Sharon Road Cincinnati, OH 45421, USA
10130600 Rev 04

Patent: EnableInjections.com/patent

Copyright © 2025 Apellis Pharmaceuticals, Inc. All rights reserved.
APELLIS, APELLISASSIST, EMPAVELI, and their respective logos are registered trademarks of Apellis Pharmaceuticals, Inc.
This Instructions for Use has been approved by the U.S. Food and Drug Administration.
Revised: 7/2025

EMP INJ-IFU-28Jul2025-2.0

PRINCIPAL DISPLAY PANEL - 1,080 mg/20 mL Vial Carton

NDC 73606-010-01

EMPAVELI®
(pegcetacoplan)
Injection

1,080 mg/20 mL
(54 mg/mL)

For Subcutaneous Infusion Only

Dispense the enclosed
Medication Guide to each patient.

One 20 mL Single-Dose Vial.
Discard unused portion.

Rx only
Apellis

PRINCIPAL DISPLAY PANEL - 20 mL Injector Carton

EMPAVELI® Injector
(pegcetacoplan)

20 mL

Single-use only
Contains NO DRUG PRODUCT

QTY 1

REF 30129903

Rx Only
Apellis